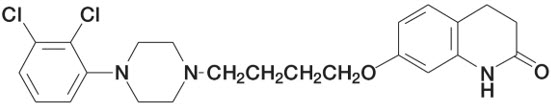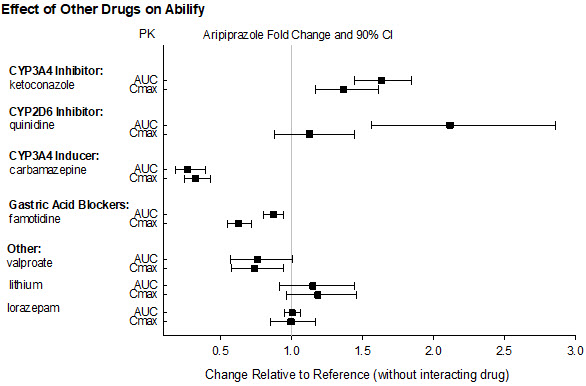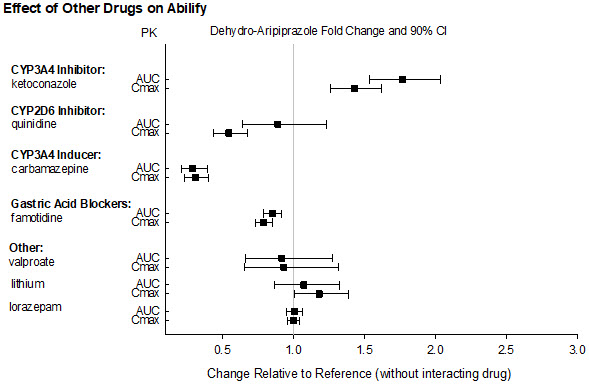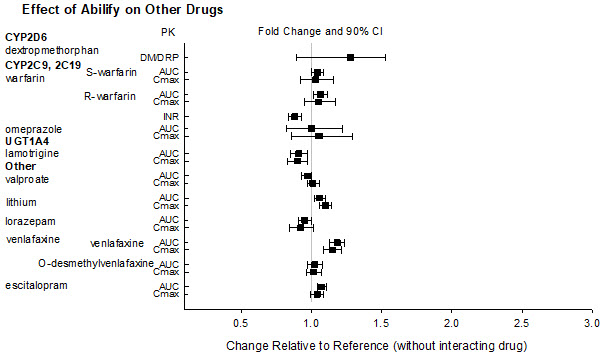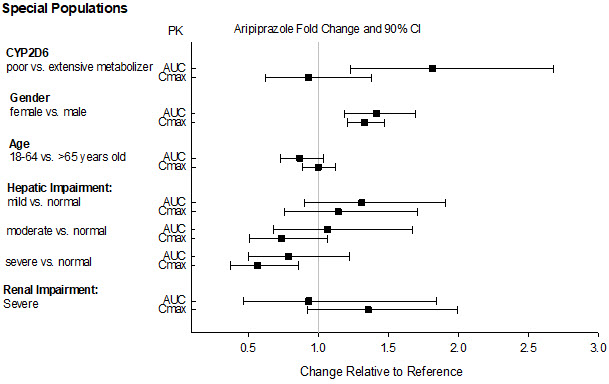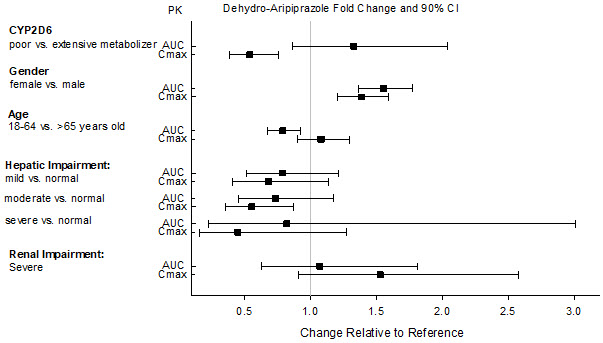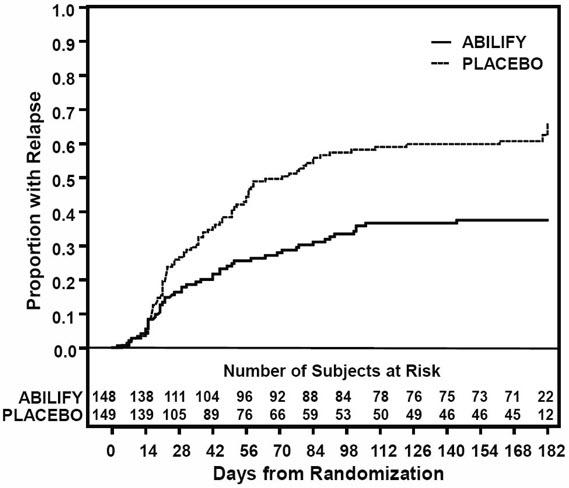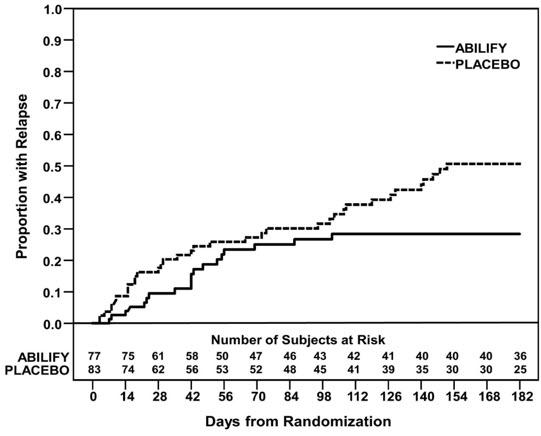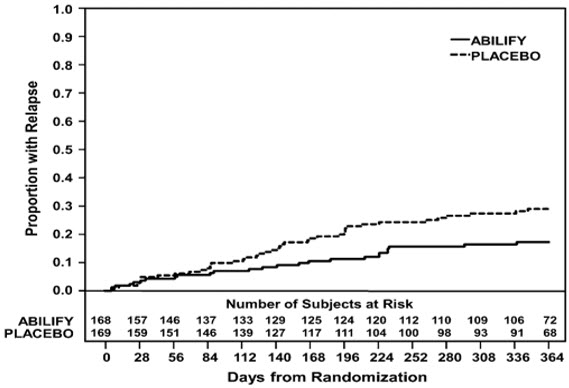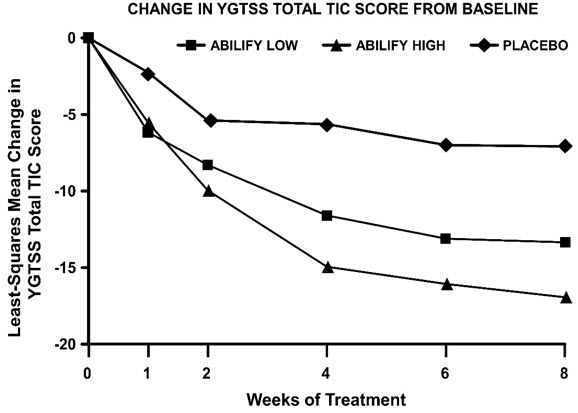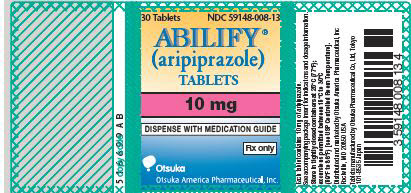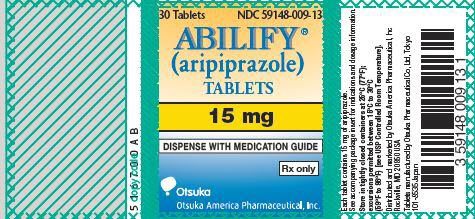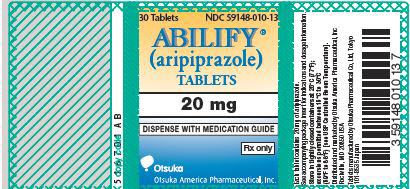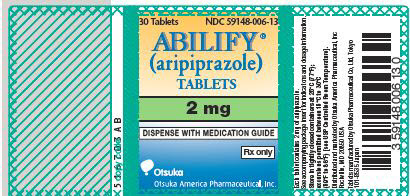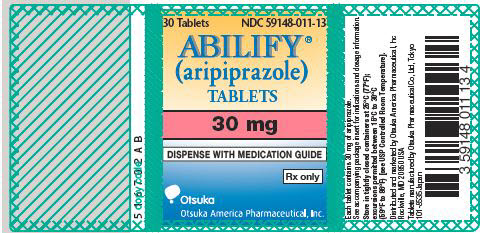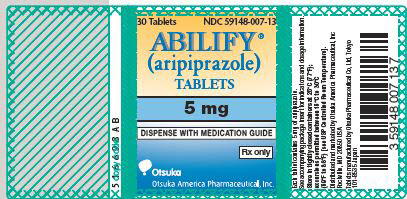 DRUG LABEL: ABILIFY
NDC: 59148-006 | Form: TABLET
Manufacturer: Otsuka America Pharmaceutical, Inc.
Category: prescription | Type: HUMAN PRESCRIPTION DRUG LABEL
Date: 20250129

ACTIVE INGREDIENTS: ARIPIPRAZOLE 2 mg/1 1
INACTIVE INGREDIENTS: STARCH, CORN; HYDROXYPROPYL CELLULOSE (1600000 WAMW); LACTOSE MONOHYDRATE; MAGNESIUM STEARATE; MICROCRYSTALLINE CELLULOSE; FERRIC OXIDE YELLOW; FD&C BLUE NO. 2 ALUMINUM LAKE

HIGHLIGHTS OF PRESCRIBING INFORMATION

These highlights do not include all the information needed to use ABILIFY safely and effectively. See full prescribing information for ABILIFY.
ABILIFY® (aripiprazole) Tablets, for oral use
Initial U.S. Approval: 2002

WARNING: INCREASED MORTALITY IN ELDERLY PATIENTS WITH DEMENTIA-RELATED PSYCHOSIS and SUICIDAL THOUGHTS AND BEHAVIORS WITH ANTIDEPRESSANT DRUGS

See full prescribing information for complete boxed warning.

- Elderly patients with dementia-related psychosis treated with antipsychotic drugs are at an increased risk of death. ABILIFY is not approved for the treatment of patients with dementia-related psychosis. (5.1)
- Increased risk of suicidal thinking and behavior in children, adolescents, and young adults taking antidepressants. Monitor for worsening and emergence of suicidal thoughts and behaviors. (5.3)

RECENT MAJOR CHANGES

Indications and Usage (1) | 1/2025
Dosage and Administration
Agitation Associated with Schizophrenia or Bipolar Mania (Intramuscular Injection) (2.6) | Removed 1/2025
Dosing of Oral Solution (2.8) | Removed 1/2025
Dosing of Orally Disintegrating Tablet (2.9) | Removed 1/2025
Warnings and Precautions
Orthostatic Hypotension (5.8) | 1/2025
Seizures/Convulsions (5.11) | 1/2025
Potential for Cognitive and Motor Impairment (5.12) | 1/2025

1 INDICATIONS AND USAGE

ABILIFY is an atypical antipsychotic. ABILIFY is indicated for:

- Schizophrenia (14.1)
- Acute Treatment of Manic and Mixed Episodes associated with Bipolar I Disorder (14.2)
- Adjunctive Treatment of Major Depressive Disorder (14.3)
- Irritability Associated with Autistic Disorder (14.4)
- Treatment of Tourette's Disorder (14.5)

2 DOSAGE AND ADMINISTRATION

- Administer once daily without regard to meals (2)

 |  | Initial Dose | Recommended Dose | Maximum Dose
Schizophrenia – adults (2.1) |  | 10 to 15 mg/day | 10 to 15 mg/day | 30 mg/day
Schizophrenia – adolescents (2.1) |  | 2 mg/day | 10 mg/day | 30 mg/day
Bipolar mania – adults: monotherapy (2.2) |  | 15 mg/day | 15 mg/day | 30 mg/day
Bipolar mania – adults: adjunct to lithium or valproate (2.2) |  | 10 to 15 mg/day | 15 mg/day | 30 mg/day
Bipolar mania – pediatric patients: monotherapy or as an adjunct to lithium or valproate (2.2) |  | 2 mg/day | 10 mg/day | 30 mg/day
Major Depressive Disorder – adults: adjunct to antidepressants (2.3) |  | 2 to 5 mg/day | 5 to 10 mg/day | 15 mg/day
Irritability associated with autistic disorder – pediatric patients (2.4) |  | 2 mg/day | 5 to 10 mg/day | 15 mg/day
Tourette's Disorder – (2.5) | Patients <50 kg | 2 mg/day | 5 mg/day | 10 mg/day
Tourette's Disorder – (2.5) | Patients ≥50 kg | 2 mg/day | 10 mg/day | 20 mg/day

- Known CYP2D6 poor metabolizers: Half of the usual dose (2.6)

3 DOSAGE FORMS AND STRENGTHS

- Tablets: 2 mg, 5 mg, 10 mg, 15 mg, 20 mg, and 30 mg (3)

4 CONTRAINDICATIONS

- Known hypersensitivity to ABILIFY (4)

5 WARNINGS AND PRECAUTIONS

- Cerebrovascular Adverse Reactions in Elderly Patients with Dementia-Related Psychosis: Increased incidence of cerebrovascular adverse reactions (e.g., stroke, transient ischemic attack, including fatalities) (5.1, 5.2)
- Neuroleptic Malignant Syndrome: Manage with immediate discontinuation and close monitoring (5.4)
- Tardive Dyskinesia: Discontinue if clinically appropriate (5.5)
- Metabolic Changes: Atypical antipsychotic drugs have been associated with metabolic changes that include hyperglycemia/diabetes mellitus, dyslipidemia, and body weight gain (5.6)
  - Hyperglycemia/Diabetes Mellitus: Monitor glucose regularly in patients with and at risk for diabetes (5.6)
  - Dyslipidemia: Undesirable alterations in lipid levels have been observed in patients treated with atypical antipsychotics (5.6)
  - Weight Gain: Weight gain has been observed with atypical antipsychotic use. Monitor weight (5.6)
- Pathological Gambling and Other Compulsive Behaviors: Consider dose reduction or discontinuation (5.7)
- Orthostatic Hypotension: Monitor heart rate and blood pressure and warn patients with known cardiovascular or cerebrovascular disease, and risk of dehydration or syncope (5.8)
- Leukopenia, Neutropenia, and Agranulocytosis: have been reported with antipsychotics including ABILIFY. Patients with a history of a clinically significant low white blood cell count (WBC) or a drug-induced leukopenia/neutropenia should have their complete blood count (CBC) monitored frequently during the first few months of therapy and discontinuation of ABILIFY should be considered at the first sign of a clinically significant decline in WBC in the absence of other causative factors (5.10)
- Seizures/Convulsions: Use cautiously in patients with a history of seizures or with conditions that lower the seizure threshold (5.11)
- Potential for Cognitive and Motor Impairment: Use caution when operating machinery (5.12)
- Suicide: The possibility of a suicide attempt is inherent in schizophrenia and bipolar disorder. Closely supervise high-risk patients (5.14)

6 ADVERSE REACTIONS

Commonly observed adverse reactions (incidence ≥5% and at least twice that for placebo) were (6.1):

- Adult patients with schizophrenia: akathisia
- Pediatric patients (13 to 17 years) with schizophrenia: extrapyramidal disorder, somnolence, and tremor
- Adult patients (monotherapy) with bipolar mania: akathisia, sedation, restlessness, tremor, and extrapyramidal disorder
- Adult patients (adjunctive therapy with lithium or valproate) with bipolar mania: akathisia, insomnia, and extrapyramidal disorder
- Pediatric patients (10 to 17 years) with bipolar mania: somnolence, extrapyramidal disorder, fatigue, nausea, akathisia, blurred vision, salivary hypersecretion, and dizziness
- Adult patients with major depressive disorder (adjunctive treatment to antidepressant therapy): akathisia, restlessness, insomnia, constipation, fatigue, and blurred vision
- Pediatric patients (6 to 17 years) with autistic disorder: sedation, fatigue, vomiting, somnolence, tremor, pyrexia, drooling, decreased appetite, salivary hypersecretion, extrapyramidal disorder, and lethargy
- Pediatric patients (6 to 18 years) with Tourette's Disorder: sedation, somnolence, nausea, headache, nasopharyngitis, fatigue, increased appetite

To report SUSPECTED ADVERSE REACTIONS, contact Otsuka America Pharmaceutical, Inc. at 1-800-438-9927 or FDA at 1-800-FDA-1088 or www.fda.gov/medwatch.

7 DRUG INTERACTIONS

Dosage adjustment due to drug interactions (7.1):

Factors | Dosage Adjustments for ABILIFY
Known CYP2D6 Poor Metabolizers | Administer half of usual dose
Known CYP2D6 Poor Metabolizers and strong CYP3A4 inhibitors | Administer a quarter of usual dose
Strong CYP2D6 or CYP3A4 inhibitors | Administer half of usual dose
Strong CYP2D6 and CYP3A4 inhibitors | Administer a quarter of usual dose
Strong CYP3A4 inducers | Double usual dose over 1 to 2 weeks

8 USE IN SPECIFIC POPULATIONS

Pregnancy: May cause extrapyramidal and/or withdrawal symptoms in neonates with third trimester exposure (8.1)

Lactation: Monitor the breastfed infant for dehydration and lack of appropriate weight gain (8.2)

FULL PRESCRIBING INFORMATION

WARNING: INCREASED MORTALITY IN ELDERLY PATIENTS WITH DEMENTIA-RELATED PSYCHOSIS and SUICIDAL THOUGHTS AND BEHAVIORS WITH ANTIDEPRESSANT DRUGS

Elderly patients with dementia-related psychosis treated with antipsychotic drugs are at an increased risk of death. ABILIFY is not approved for the treatment of patients with dementia-related psychosis [see Warnings and Precautions (5.1)].

Antidepressants increased the risk of suicidal thoughts and behavior in children, adolescents, and young adults in short-term studies. These studies did not show an increase in the risk of suicidal thoughts and behavior with antidepressant use in patients over age 24 years; there was a reduction in risk with antidepressant use in patients aged 65 years and older [see Warnings and Precautions (5.3)].

In patients of all ages who are started on antidepressant therapy, monitor closely for worsening, and for emergence of suicidal thoughts and behaviors. Advise families and caregivers of the need for close observation and communication with the prescriber [see Warnings and Precautions (5.3)].

1 INDICATIONS AND USAGE

ABILIFY (aripiprazole) Tablets are indicated for the treatment of:

- Schizophrenia
- Acute Treatment of Manic and Mixed Episodes associated with Bipolar I Disorder
- Adjunctive Treatment of Major Depressive Disorder
- Irritability Associated with Autistic Disorder
- Treatment of Tourette's Disorder

2 DOSAGE AND ADMINISTRATION

2.1 Schizophrenia

Adults

The recommended starting and target dose for ABILIFY is 10 or 15 mg/day administered on a once-a-day schedule without regard to meals. ABILIFY has been systematically evaluated and shown to be effective in a dose range of 10 to 30 mg/day, when administered as the tablet formulation; however, doses higher than 10 or 15 mg/day were not more effective than 10 or 15 mg/day. Dosage increases should generally not be made before 2 weeks, the time needed to achieve steady-state [see Clinical Studies (14.1)].

Maintenance Treatment: Maintenance of efficacy in schizophrenia was demonstrated in a trial involving patients with schizophrenia who had been symptomatically stable on other antipsychotic medications for periods of 3 months or longer. These patients were discontinued from those medications and randomized to either ABILIFY 15 mg/day or placebo and observed for relapse [see Clinical Studies (14.1)]. Patients should be periodically reassessed to determine the continued need for maintenance treatment.

Adolescents

The recommended target dose of ABILIFY is 10 mg/day. Aripiprazole was studied in adolescent patients 13 to 17 years of age with schizophrenia at daily doses of 10 and 30 mg. The starting daily dose of the tablet formulation in these patients was 2 mg, which was titrated to 5 mg after 2 days and to the target dose of 10 mg after 2 additional days. Subsequent dose increases should be administered in 5 mg increments. The 30 mg/day dose was not shown to be more efficacious than the 10 mg/day dose. ABILIFY can be administered without regard to meals [see Clinical Studies (14.1)]. Patients should be periodically reassessed to determine the need for maintenance treatment.

Switching from Other Antipsychotics

There are no systematically collected data to specifically address switching patients with schizophrenia from other antipsychotics to ABILIFY or concerning concomitant administration with other antipsychotics. While immediate discontinuation of the previous antipsychotic treatment may be acceptable for some patients with schizophrenia, more gradual discontinuation may be most appropriate for others. In all cases, the period of overlapping antipsychotic administration should be minimized.

2.2 Bipolar I Disorder

Acute Treatment of Manic and Mixed Episodes

Adults: The recommended starting dose in adults is 15 mg given once daily as monotherapy and 10 mg to 15 mg given once daily as adjunctive therapy with lithium or valproate. ABILIFY can be given without regard to meals. The recommended target dose of ABILIFY is 15 mg/day, as monotherapy or as adjunctive therapy with lithium or valproate. The dose may be increased to 30 mg/day based on clinical response. The safety of doses above 30 mg/day has not been evaluated in clinical trials.

Pediatrics: The recommended starting dose in pediatric patients (10 to 17 years) as monotherapy is 2 mg/day, with titration to 5 mg/day after 2 days, and a target dose of 10 mg/day after 2 additional days. Recommended dosing as adjunctive therapy to lithium or valproate is the same. Subsequent dose increases, if needed, should be administered in 5 mg/day increments. ABILIFY can be given without regard to meals [see Clinical Studies (14.2)].

2.3 Adjunctive Treatment of Major Depressive Disorder

Adults

The recommended starting dose for ABILIFY as adjunctive treatment for patients already taking an antidepressant is 2 to 5 mg/day. The recommended dosage range is 2 to 15 mg/day. Dosage adjustments of up to 5 mg/day should occur gradually, at intervals of no less than one week [see Clinical Studies (14.3)]. Patients should be periodically reassessed to determine the continued need for maintenance treatment.

2.4 Irritability Associated with Autistic Disorder

Pediatric Patients (6 to 17 years)

The recommended dosage range for the treatment of pediatric patients with irritability associated with autistic disorder is 5 to 15 mg/day.

Dosing should be initiated at 2 mg/day. The dose should be increased to 5 mg/day, with subsequent increases to 10 or 15 mg/day if needed. Dose adjustments of up to 5 mg/day should occur gradually, at intervals of no less than one week [see Clinical Studies (14.4)]. Patients should be periodically reassessed to determine the continued need for maintenance treatment.

2.5 Tourette's Disorder

Pediatric Patients (6 to 18 years)

The recommended dosage range for Tourette's Disorder is 5 to 20 mg/day.

For patients weighing less than 50 kg, dosing should be initiated at 2 mg/day with a target dose of 5 mg/day after 2 days. The dose can be increased to 10 mg/day in patients who do not achieve optimal control of tics. Dosage adjustments should occur gradually at intervals of no less than one week.

For patients weighing 50 kg or more, dosing should be initiated at 2 mg/day for 2 days, and then increased to 5 mg/day for 5 days, with a target dose of 10 mg/day on Day 8. The dose can be increased up to 20 mg/day for patients who do not achieve optimal control of tics. Dosage adjustments should occur gradually in increments of 5 mg/day at intervals of no less than one week [see Clinical Studies (14.5)].

Patients should be periodically reassessed to determine the continued need for maintenance treatment.

2.6 Dosage Adjustments for Cytochrome P450 Considerations

Dosage adjustments are recommended in patients who are known CYP2D6 poor metabolizers and in patients taking concomitant CYP3A4 inhibitors or CYP2D6 inhibitors or strong CYP3A4 inducers (see Table 1). When the coadministered drug is withdrawn from the combination therapy, ABILIFY dosage should then be adjusted to its original level. When the coadministered CYP3A4 inducer is withdrawn, ABILIFY dosage should be reduced to the original level over 1 to 2 weeks. Patients who may be receiving a combination of strong, moderate, and weak inhibitors of CYP3A4 and CYP2D6 (e.g., a strong CYP3A4 inhibitor and a moderate CYP2D6 inhibitor or a moderate CYP3A4 inhibitor with a moderate CYP2D6 inhibitor), the dosing may be reduced to one-quarter (25%) of the usual dose initially and then adjusted to achieve a favorable clinical response.

Table 1: Dose Adjustments for ABILIFY in Patients who are known CYP2D6 Poor Metabolizers and Patients Taking Concomitant CYP2D6 Inhibitors, CYP3A4 Inhibitors, and/or CYP3A4 Inducers
Factors | Dosage Adjustments for ABILIFY
Known CYP2D6 Poor Metabolizers | Administer half of usual dose
Known CYP2D6 Poor Metabolizers taking concomitant strong CYP3A4 inhibitors (e.g., itraconazole, clarithromycin) | Administer a quarter of usual dose
Strong CYP2D6 (e.g., quinidine, fluoxetine, paroxetine) or CYP3A4 inhibitors (e.g., itraconazole, clarithromycin) | Administer half of usual dose
Strong CYP2D6 and CYP3A4 inhibitors | Administer a quarter of usual dose
Strong CYP3A4 inducers (e.g., carbamazepine, rifampin) | Double usual dose over 1 to 2 weeks

When adjunctive ABILIFY is administered to patients with major depressive disorder, ABILIFY should be administered without dosage adjustment as specified in Dosage and Administration (2.3).

3 DOSAGE FORMS AND STRENGTHS

ABILIFY® (aripiprazole) Tablets are available as described in Table 2.

Table 2: ABILIFY Tablet Presentations
Tablet Strength | Tablet Color/Shape | Tablet Markings
2 mg | green modified rectangle | "A-006" and "2"
5 mg | blue modified rectangle | "A-007" and "5"
10 mg | pink modified rectangle | "A-008" and "10"
15 mg | yellow round | "A-009" and "15"
20 mg | white round | "A-010" and "20"
30 mg | pink round | "A-011" and "30"

4 CONTRAINDICATIONS

ABILIFY is contraindicated in patients with a history of a hypersensitivity reaction to aripiprazole. Reactions have ranged from pruritus/urticaria to anaphylaxis [see Adverse Reactions (6.2)].

5 WARNINGS AND PRECAUTIONS

5.1 Increased Mortality in Elderly Patients with Dementia-Related Psychosis

Increased Mortality

Elderly patients with dementia-related psychosis treated with antipsychotic drugs are at an increased risk of death. ABILIFY (aripiprazole) is not approved for the treatment of patients with dementia-related psychosis [see Boxed Warning].

Safety Experience in Elderly Patients with Psychosis Associated with Alzheimer's Disease

In three, 10-week, placebo-controlled studies of ABILIFY in elderly patients with psychosis associated with Alzheimer's disease (n=938; mean age: 82.4 years; range: 56 to 99 years), the adverse reactions that were reported at an incidence of ≥3% and ABILIFY incidence at least twice that for placebo were lethargy [placebo 2%, ABILIFY 5%], somnolence (including sedation) [placebo 3%, ABILIFY 8%], and incontinence (primarily, urinary incontinence) [placebo 1%, ABILIFY 5%], excessive salivation [placebo 0%, ABILIFY 4%], and lightheadedness [placebo 1%, ABILIFY 4%].

The safety and efficacy of ABILIFY in the treatment of patients with psychosis associated with dementia have not been established. If the prescriber elects to treat such patients with ABILIFY, assess for the emergence of difficulty swallowing or excessive somnolence, which could predispose to accidental injury or aspiration [see Boxed Warning].

5.2 Cerebrovascular Adverse Events, Including Stroke

In placebo-controlled clinical studies (two flexible dose and one fixed dose study) of dementia-related psychosis, there was an increased incidence of cerebrovascular adverse events (e.g., stroke, transient ischemic attack), including fatalities, in ABILIFY-treated patients (mean age: 84 years; range: 78 to 88 years). In the fixed-dose study, there was a statistically significant dose response relationship for cerebrovascular adverse events in patients treated with ABILIFY. ABILIFY is not approved for the treatment of patients with dementia-related psychosis [see Boxed Warning].

5.3 Suicidal Thoughts and Behaviors in Children, Adolescents, and Young Adults

Patients with major depressive disorder (MDD), both adult and pediatric, may experience worsening of their depression and/or the emergence of suicidal ideation and behavior (suicidality) or unusual changes in behavior, whether or not they are taking antidepressant medications, and this risk may persist until significant remission occurs. Suicide is a known risk of depression and certain other psychiatric disorders, and these disorders themselves are the strongest predictors of suicide. There has been a long-standing concern, however, that antidepressants may have a role in inducing worsening of depression and the emergence of suicidality in certain patients during the early phases of treatment. Pooled analyses of short-term, placebo-controlled trials of antidepressant drugs (SSRIs and others) showed that these drugs increase the risk of suicidal thinking and behavior (suicidality) in children, adolescents, and young adults (ages 18 to 24 years) with MDD and other psychiatric disorders. Short-term studies did not show an increase in the risk of suicidality with antidepressants compared to placebo in adults beyond age 24 years; there was a reduction with antidepressants compared to placebo in adults aged 65 years and older.

The pooled analyses of placebo-controlled trials in children and adolescents with MDD, Obsessive Compulsive Disorder (OCD), or other psychiatric disorders included a total of 24 short-term trials of 9 antidepressant drugs in over 4400 patients. The pooled analyses of placebo-controlled trials in adults with MDD or other psychiatric disorders included a total of 295 short-term trials (median duration of 2 months) of 11 antidepressant drugs in over 77,000 patients. There was considerable variation in risk of suicidality among drugs, but a tendency toward an increase in the younger patients for almost all drugs studied. There were differences in absolute risk of suicidality across the different indications, with the highest incidence in MDD. The risk differences (drug vs. placebo), however, were relatively stable within age strata and across indications. These risk differences (drug-placebo difference in the number of cases of suicidality per 1,000 patients treated) are provided in Table 3.

Table 3:
Age Range | Drug-Placebo Difference in Number of Cases of Suicidality per 1000 Patients Treated
Increases Compared to Placebo
<18 | 14 additional cases
18 to 24 | 5 additional cases
Decreases Compared to Placebo
25 to 64 | 1 fewer case
≥65 | 6 fewer cases

No suicides occurred in any of the pediatric trials. There were suicides in the adult trials, but the number was not sufficient to reach any conclusion about drug effect on suicide.

It is unknown whether the suicidality risk extends to longer-term use, i.e., beyond several months. However, there is substantial evidence from placebo-controlled maintenance trials in adults with depression that the use of antidepressants can delay the recurrence of depression.

All patients being treated with antidepressants for any indication should be monitored appropriately and observed closely for clinical worsening, suicidality, and unusual changes in behavior, especially during the initial few months of a course of drug therapy, or at times of dose changes, either increases or decreases.

The following symptoms, anxiety, agitation, panic attacks, insomnia, irritability, hostility, aggressiveness, impulsivity, akathisia (psychomotor restlessness), hypomania, and mania, have been reported in adult and pediatric patients being treated with antidepressants for MDD as well as for other indications, both psychiatric and nonpsychiatric. Although a causal link between the emergence of such symptoms and either the worsening of depression and/or the emergence of suicidal impulses has not been established, there is concern that such symptoms may represent precursors to emerging suicidality.

Consideration should be given to changing the therapeutic regimen, including possibly discontinuing the medication, in patients whose depression is persistently worse, or who are experiencing emergent suicidality or symptoms that might be precursors to worsening depression or suicidality, especially if these symptoms are severe, abrupt in onset, or were not part of the patient's presenting symptoms.

Families and caregivers of patients being treated with antidepressants for major depressive disorder or other indications, both psychiatric and nonpsychiatric, should be alerted about the need to monitor patients for the emergence of agitation, irritability, unusual changes in behavior, and the other symptoms described above, as well as the emergence of suicidality, and to report such symptoms immediately to healthcare providers. Such monitoring should include daily observation by families and caregivers. Prescriptions for ABILIFY should be written for the smallest quantity of tablets consistent with good patient management, in order to reduce the risk of overdose.

Screening Patients for Bipolar Disorder: A major depressive episode may be the initial presentation of bipolar disorder. It is generally believed (though not established in controlled trials) that treating such an episode with an antidepressant alone may increase the likelihood of precipitation of a mixed/manic episode in patients at risk for bipolar disorder. Whether any of the symptoms described above represent such a conversion is unknown. However, prior to initiating treatment with an antidepressant, patients with depressive symptoms should be adequately screened to determine if they are at risk for bipolar disorder; such screening should include a detailed psychiatric history, including a family history of suicide, bipolar disorder, and depression.

It should be noted that ABILIFY is not approved for use in treating depression in the pediatric population.

5.4 Neuroleptic Malignant Syndrome (NMS)

A potentially fatal symptom complex sometimes referred to as Neuroleptic Malignant Syndrome (NMS) may occur with administration of antipsychotic drugs, including ABILIFY. Rare cases of NMS occurred during ABILIFY treatment in the worldwide clinical database. Clinical manifestations of NMS are hyperpyrexia, muscle rigidity, altered mental status, and evidence of autonomic instability (irregular pulse or blood pressure, tachycardia, diaphoresis, and cardiac dysrhythmia). Additional signs may include elevated creatine phosphokinase, myoglobinuria (rhabdomyolysis), and acute renal failure.

The diagnostic evaluation of patients with this syndrome is complicated. In arriving at a diagnosis, it is important to exclude cases where the clinical presentation includes both serious medical illness (e.g., pneumonia, systemic infection) and untreated or inadequately treated extrapyramidal signs and symptoms (EPS). Other important considerations in the differential diagnosis include central anticholinergic toxicity, heat stroke, drug fever, and primary central nervous system (CNS) pathology.

The management of NMS should include: 1) immediate discontinuation of antipsychotic drugs and other drugs not essential to concurrent therapy; 2) intensive symptomatic treatment and medical monitoring; and 3) treatment of any concomitant serious medical problems for which specific treatments are available. There is no general agreement about specific pharmacological treatment regimens for uncomplicated NMS.

If a patient requires antipsychotic drug treatment after recovery from NMS, the potential reintroduction of drug therapy should be carefully considered. The patient should be carefully monitored since recurrences of NMS have been reported.

5.5 Tardive Dyskinesia

A syndrome of potentially irreversible, involuntary, dyskinetic movements may develop in patients treated with antipsychotic drugs. Although the prevalence of the syndrome appears to be highest among the elderly, especially elderly women, it is impossible to rely upon prevalence estimates to predict, at the inception of antipsychotic treatment, which patients are likely to develop the syndrome. Whether antipsychotic drug products differ in their potential to cause tardive dyskinesia is unknown.

The risk of developing tardive dyskinesia and the likelihood that it will become irreversible are believed to increase as the duration of treatment and the total cumulative dose of antipsychotic drugs administered to the patient increase. However, the syndrome can develop, although much less commonly, after relatively brief treatment periods at low doses.

Tardive dyskinesia may remit, partially or completely, if antipsychotic treatment is withdrawn. Antipsychotic treatment, itself, however, may suppress (or partially suppress) the signs and symptoms of the syndrome and, thereby, may possibly mask the underlying process. The effect that symptomatic suppression has upon the long-term course of the syndrome is unknown.

Given these considerations, ABILIFY should be prescribed in a manner that is most likely to minimize the occurrence of tardive dyskinesia. Chronic antipsychotic treatment should generally be reserved for patients who suffer from a chronic illness that (1) is known to respond to antipsychotic drugs and (2) for whom alternative, equally effective, but potentially less harmful treatments are not available or appropriate. In patients who do require chronic treatment, the smallest dose and the shortest duration of treatment producing a satisfactory clinical response should be sought. The need for continued treatment should be reassessed periodically.

If signs and symptoms of tardive dyskinesia appear in a patient on ABILIFY, drug discontinuation should be considered. However, some patients may require treatment with ABILIFY despite the presence of the syndrome.

5.6 Metabolic Changes

Atypical antipsychotic drugs have been associated with metabolic changes that include hyperglycemia/diabetes mellitus, dyslipidemia, and body weight gain. While all drugs in the class have been shown to produce some metabolic changes, each drug has its own specific risk profile.

Hyperglycemia/Diabetes Mellitus

Hyperglycemia, in some cases extreme and associated with ketoacidosis or hyperosmolar coma or death, has been reported in patients treated with atypical antipsychotics. There have been reports of hyperglycemia in patients treated with ABILIFY [see Adverse Reactions (6.1, 6.2)]. Assessment of the relationship between atypical antipsychotic use and glucose abnormalities is complicated by the possibility of an increased background risk of diabetes mellitus in patients with schizophrenia and the increasing incidence of diabetes mellitus in the general population. Given these confounders, the relationship between atypical antipsychotic use and hyperglycemia-related adverse events is not completely understood. However, epidemiological studies suggest an increased risk of hyperglycemia-related adverse reactions in patients treated with the atypical antipsychotics. Because ABILIFY was not marketed at the time these studies were performed, it is not known if ABILIFY is associated with this increased risk. Precise risk estimates for hyperglycemia-related adverse reactions in patients treated with atypical antipsychotics are not available.

Patients with an established diagnosis of diabetes mellitus who are started on atypical antipsychotics should be monitored regularly for worsening of glucose control. Patients with risk factors for diabetes mellitus (e.g., obesity, family history of diabetes) who are starting treatment with atypical antipsychotics should undergo fasting blood glucose testing at the beginning of treatment and periodically during treatment. Any patient treated with atypical antipsychotics should be monitored for symptoms of hyperglycemia including polydipsia, polyuria, polyphagia, and weakness. Patients who develop symptoms of hyperglycemia during treatment with atypical antipsychotics should undergo fasting blood glucose testing. In some cases, hyperglycemia has resolved when the atypical antipsychotic was discontinued; however, some patients required continuation of anti-diabetic treatment despite discontinuation of the suspect drug.

Adults

In an analysis of 13, placebo-controlled, monotherapy trials in adults, primarily with schizophrenia or bipolar disorder, the mean change in fasting glucose in ABILIFY-treated patients (+4.4 mg/dL; median exposure 25 days; N=1,057) was not significantly different than in placebo-treated patients (+2.5 mg/dL; median exposure 22 days; N=799). Table 4 shows the proportion of ABILIFY-treated patients with normal and borderline fasting glucose at baseline (median exposure 25 days) that had treatment-emergent high fasting glucose measurements compared to placebo-treated patients (median exposure 22 days).

Table 4: Changes in Fasting Glucose from Placebo-Controlled Monotherapy Trials in Adult Patients
 | Category Change (at least once) from Baseline | Treatment Arm | n/N | %
Fasting Glucose | Normal to High (<100 mg/dL to ≥126 mg/dL) | ABILIFY | 31/822 | 3.8
Fasting Glucose | Normal to High (<100 mg/dL to ≥126 mg/dL) | Placebo | 22/605 | 3.6
Fasting Glucose | Borderline to High (≥100 mg/dL and <126 mg/dL to ≥126 mg/dL) | ABILIFY | 31/176 | 17.6
Fasting Glucose | Borderline to High (≥100 mg/dL and <126 mg/dL to ≥126 mg/dL) | Placebo | 13/142 | 9.2

At 24 weeks, the mean change in fasting glucose in ABILIFY-treated patients was not significantly different than in placebo-treated patients [+2.2 mg/dL (n=42) and +9.6 mg/dL (n=28), respectively].

The mean change in fasting glucose in adjunctive ABILIFY-treated patients with major depressive disorder (+0.7 mg/dL; median exposure 42 days; N=241) was not significantly different than in placebo-treated patients (+0.8 mg/dL; median exposure 42 days; N=246). Table 5 shows the proportion of adult patients with changes in fasting glucose levels from two placebo-controlled, adjunctive trials (median exposure 42 days) in patients with major depressive disorder.

Table 5: Changes in Fasting Glucose from Placebo-Controlled Adjunctive Trials in Adult Patients with Major Depressive Disorder
 | Category Change (at least once) from Baseline | Treatment Arm | n/N | %
Fasting Glucose | Normal to High (<100 mg/dL to ≥126 mg/dL) | ABILIFY | 2/201 | 1.0
Fasting Glucose | Normal to High (<100 mg/dL to ≥126 mg/dL) | Placebo | 2/204 | 1.0
Fasting Glucose | Borderline to High (≥100 mg/dL and <126 mg/dL to ≥126 mg/dL) | ABILIFY | 4/34 | 11.8
Fasting Glucose | Borderline to High (≥100 mg/dL and <126 mg/dL to ≥126 mg/dL) | Placebo | 3/37 | 8.1

Pediatric Patients and Adolescents

In an analysis of two placebo-controlled trials in adolescents with schizophrenia (13 to 17 years) and pediatric patients with bipolar disorder (10 to 17 years), the mean change in fasting glucose in ABILIFY-treated patients (+4.8 mg/dL; with a median exposure of 43 days; N=259) was not significantly different than in placebo-treated patients (+1.7 mg/dL; with a median exposure of 42 days; N=123).

In an analysis of two placebo-controlled trials in pediatric and adolescent patients with irritability associated with autistic disorder (6 to 17 years) with median exposure of 56 days, the mean change in fasting glucose in ABILIFY-treated patients (–0.2 mg/dL; N=83) was not significantly different than in placebo-treated patients (–0.6 mg/dL; N=33).

In an analysis of two placebo-controlled trials in pediatric and adolescent patients with Tourette's Disorder (6 to 18 years) with median exposure of 57 days, the mean change in fasting glucose in ABILIFY-treated patients (0.79 mg/dL; N=90) was not significantly different than in placebo-treated patients (–1.66 mg/dL; N=58).

Table 6 shows the proportion of patients with changes in fasting glucose levels from the pooled adolescent schizophrenia and pediatric bipolar patients (median exposure of 42 to 43 days), from two placebo-controlled trials in pediatric patients (6 to 17 years) with irritability associated with autistic disorder (median exposure of 56 days), and from the two placebo-controlled trials in pediatric patients (6 to 18 year) with Tourette's Disorder (median exposure 57 days).

Table 6: Changes in Fasting Glucose from Placebo-Controlled Trials in Pediatric and Adolescent Patients
Category Change (at least once) from Baseline | Indication | Treatment Arm | n/N | %
Fasting Glucose Normal to High (<100 mg/dL to ≥126 mg/dL) | Pooled Schizophrenia and Bipolar Disorder | ABILIFY | 2/236 | 0.8
Fasting Glucose Normal to High (<100 mg/dL to ≥126 mg/dL) | Pooled Schizophrenia and Bipolar Disorder | Placebo | 2/110 | 1.8
Fasting Glucose Normal to High (<100 mg/dL to ≥126 mg/dL) | Irritability Associated with Autistic Disorder | ABILIFY | 0/73 | 0
Fasting Glucose Normal to High (<100 mg/dL to ≥126 mg/dL) | Irritability Associated with Autistic Disorder | Placebo | 0/32 | 0
Fasting Glucose Normal to High (<100 mg/dL to ≥126 mg/dL) | Tourette's Disorder | ABILIFY | 3/88 | 3.4
Fasting Glucose Normal to High (<100 mg/dL to ≥126 mg/dL) | Tourette's Disorder | Placebo | 1/58 | 1.7
Fasting Glucose Borderline to High (≥100 mg/dL and <126mg/dL to ≥126 mg/dL) | Pooled Schizophrenia and Bipolar Disorder | ABILIFY | 1/22 | 4.5
Fasting Glucose Borderline to High (≥100 mg/dL and <126mg/dL to ≥126 mg/dL) | Pooled Schizophrenia and Bipolar Disorder | Placebo | 0/12 | 0
Fasting Glucose Borderline to High (≥100 mg/dL and <126mg/dL to ≥126 mg/dL) | Irritability Associated with Autistic Disorder | ABILIFY | 0/9 | 0
Fasting Glucose Borderline to High (≥100 mg/dL and <126mg/dL to ≥126 mg/dL) | Irritability Associated with Autistic Disorder | Placebo | 0/1 | 0
Fasting Glucose Borderline to High (≥100 mg/dL and <126mg/dL to ≥126 mg/dL) | Tourette's Disorder | ABILIFY | 0/11 | 0
Fasting Glucose Borderline to High (≥100 mg/dL and <126mg/dL to ≥126 mg/dL) | Tourette's Disorder | Placebo | 0/4 | 0

At 12 weeks in the pooled adolescent schizophrenia and pediatric bipolar disorder trials, the mean change in fasting glucose in ABILIFY-treated patients was not significantly different than in placebo-treated patients [+2.4 mg/dL (n=81) and +0.1 mg/dL (n=15), respectively].

Dyslipidemia

Undesirable alterations in lipids have been observed in patients treated with atypical antipsychotics.

There were no significant differences between ABILIFY- and placebo-treated patients in the proportion with changes from normal to clinically significant levels for fasting/nonfasting total cholesterol, fasting triglycerides, fasting LDLs, and fasting/nonfasting HDLs. Analyses of patients with at least 12 or 24 weeks of exposure were limited by small numbers of patients.

Adults

Table 7 shows the proportion of adult patients, primarily from pooled, schizophrenia and bipolar disorder, monotherapy, placebo-controlled trials, with changes in total cholesterol (pooled from 17 trials; median exposure 21 to 25 days), fasting triglycerides (pooled from eight trials; median exposure 42 days), fasting LDL cholesterol (pooled from eight trials; median exposure 39 to 45 days, except for placebo-treated patients with baseline normal fasting LDL measurements, who had median treatment exposure of 24 days) and HDL cholesterol (pooled from nine trials; median exposure 40 to 42 days).

Table 7: Changes in Blood Lipid Parameters from Placebo-Controlled Monotherapy Trials in Adults
 | Treatment Arm | n/N | %
Total Cholesterol Normal to High (<200 mg/dL to ≥240 mg/dL) | ABILIFY | 34/1,357 | 2.5
Total Cholesterol Normal to High (<200 mg/dL to ≥240 mg/dL) | Placebo | 27/973 | 2.8
Fasting Triglycerides Normal to High (<150 mg/dL to ≥200 mg/dL) | ABILIFY | 40/539 | 7.4
Fasting Triglycerides Normal to High (<150 mg/dL to ≥200 mg/dL) | Placebo | 30/431 | 7.0
Fasting LDL Cholesterol Normal to High (<100 mg/dL to ≥160 mg/dL) | ABILIFY | 2/332 | 0.6
Fasting LDL Cholesterol Normal to High (<100 mg/dL to ≥160 mg/dL) | Placebo | 2/268 | 0.7
HDL Cholesterol Normal to Low (≥40 mg/dL to <40 mg/dL) | ABILIFY | 121/1,066 | 11.4
HDL Cholesterol Normal to Low (≥40 mg/dL to <40 mg/dL) | Placebo | 99/794 | 12.5

In monotherapy trials in adults, the proportion of patients at 12 weeks and 24 weeks with changes from Normal to High in total cholesterol (fasting/nonfasting), fasting triglycerides, and fasting LDL cholesterol were similar between ABILIFY- and placebo-treated patients: at 12 weeks, Total Cholesterol (fasting/nonfasting), 1/71 (1.4%) vs. 3/74 (4.1%); Fasting Triglycerides, 8/62 (12.9%) vs. 5/37 (13.5%); Fasting LDL Cholesterol, 0/34 (0%) vs. 1/25 (4.0%), respectively; and at 24 weeks, Total Cholesterol (fasting/nonfasting), 1/42 (2.4%) vs. 3/37 (8.1%); Fasting Triglycerides, 5/34 (14.7%) vs. 5/20 (25%); Fasting LDL Cholesterol, 0/22 (0%) vs. 1/18 (5.6%), respectively.

Table 8 shows the proportion of patients with changes in total cholesterol (fasting/nonfasting), fasting triglycerides, fasting LDL cholesterol, and HDL cholesterol from two placebo-controlled adjunctive trials in adult patients with major depressive disorder (median exposure 42 days).

Table 8: Changes in Blood Lipid Parameters from Placebo-Controlled Adjunctive Trials in Adult Patients with Major Depressive Disorder
 | Treatment Arm | n/N | %
Total Cholesterol Normal to High (<200 mg/dL to ≥240 mg/dL) | ABILIFY | 3/139 | 2.2
Total Cholesterol Normal to High (<200 mg/dL to ≥240 mg/dL) | Placebo | 7/135 | 5.2
Fasting Triglycerides Normal to High (<150 mg/dL to ≥200 mg/dL) | ABILIFY | 14/145 | 9.7
Fasting Triglycerides Normal to High (<150 mg/dL to ≥200 mg/dL) | Placebo | 6/147 | 4.1
Fasting LDL Cholesterol Normal to High (<100 mg/dL to ≥160 mg/dL) | ABILIFY | 0/54 | 0
Fasting LDL Cholesterol Normal to High (<100 mg/dL to ≥160 mg/dL) | Placebo | 0/73 | 0
HDL Cholesterol Normal to Low (≥40 mg/dL to <40 mg/dL) | ABILIFY | 17/318 | 5.3
HDL Cholesterol Normal to Low (≥40 mg/dL to <40 mg/dL) | Placebo | 10/286 | 3.5

Pediatric Patients and Adolescents

Table 9 shows the proportion of adolescents with schizophrenia (13 to 17 years) and pediatric patients with bipolar disorder (10 to 17 years) with changes in total cholesterol and HDL cholesterol (pooled from two placebo-controlled trials; median exposure 42 to 43 days) and fasting triglycerides (pooled from two placebo-controlled trials; median exposure 42 to 44 days).

Table 9: Changes in Blood Lipid Parameters from Placebo-Controlled Monotherapy Trials in Pediatric and Adolescent Patients in Schizophrenia and Bipolar Disorder
 | Treatment Arm | n/N | %
Total Cholesterol Normal to High (<170 mg/dL to ≥200 mg/dL) | ABILIFY | 3/220 | 1.4
Total Cholesterol Normal to High (<170 mg/dL to ≥200 mg/dL) | Placebo | 0/116 | 0
Fasting Triglycerides Normal to High (<150 mg/dL to ≥200 mg/dL) | ABILIFY | 7/187 | 3.7
Fasting Triglycerides Normal to High (<150 mg/dL to ≥200 mg/dL) | Placebo | 4/85 | 4.7
HDL Cholesterol Normal to Low (≥40 mg/dL to <40 mg/dL) | ABILIFY | 27/236 | 11.4
HDL Cholesterol Normal to Low (≥40 mg/dL to <40 mg/dL) | Placebo | 22/109 | 20.2

In monotherapy trials of adolescents with schizophrenia and pediatric patients with bipolar disorder, the proportion of patients at 12 weeks and 24 weeks with changes from Normal to High in total cholesterol (fasting/nonfasting), fasting triglycerides, and fasting LDL cholesterol were similar between ABILIFY- and placebo-treated patients: at 12 weeks, Total Cholesterol (fasting/nonfasting), 0/57 (0%) vs. 0/15 (0%); Fasting Triglycerides, 2/72 (2.8%) vs. 1/14 (7.1%), respectively; and at 24 weeks, Total Cholesterol (fasting/nonfasting), 0/36 (0%) vs. 0/12 (0%); Fasting Triglycerides, 1/47 (2.1%) vs. 1/10 (10.0%), respectively.

Table 10 shows the proportion of patients with changes in total cholesterol (fasting/nonfasting) and fasting triglycerides (median exposure 56 days) and HDL cholesterol (median exposure 55 to 56 days) from two placebo-controlled trials in pediatric patients (6 to 17 years) with irritability associated with autistic disorder.

Table 10: Changes in Blood Lipid Parameters from Placebo-Controlled Trials in Pediatric Patients with Autistic Disorder
 | Treatment Arm | n/N | %
Total Cholesterol Normal to High (<170 mg/dL to ≥200 mg/dL) | ABILIFY | 1/95 | 1.1
Total Cholesterol Normal to High (<170 mg/dL to ≥200 mg/dL) | Placebo | 0/34 | 0
Fasting Triglycerides Normal to High (<150 mg/dL to ≥200 mg/dL) | ABILIFY | 0/75 | 0
Fasting Triglycerides Normal to High (<150 mg/dL to ≥200 mg/dL) | Placebo | 0/30 | 0
HDL Cholesterol Normal to Low (≥40 mg/dL to <40 mg/dL) | ABILIFY | 9/107 | 8.4
HDL Cholesterol Normal to Low (≥40 mg/dL to <40 mg/dL) | Placebo | 5/49 | 10.2

Table 11 shows the proportion of patients with changes in total cholesterol (fasting/nonfasting) and fasting triglycerides (median exposure 57 days) and HDL cholesterol (median exposure 57 days) from two placebo-controlled trials in pediatric patients (6 to 18 years) with Tourette's Disorder.

Table 11: Changes in Blood Lipid Parameters from Placebo-Controlled Trials in Pediatric Patients with Tourette's Disorder
 | Treatment Arm | n/N | %
Total Cholesterol Normal to High (<170 mg/dL to ≥200 mg/dL) | ABILIFY | 1/85 | 1.2
Total Cholesterol Normal to High (<170 mg/dL to ≥200 mg/dL) | Placebo | 0/46 | 0
Fasting Triglycerides Normal to High (<150 mg/dL to ≥200 mg/dL) | ABILIFY | 5/94 | 5.3
Fasting Triglycerides Normal to High (<150 mg/dL to ≥200 mg/dL) | Placebo | 2/55 | 3.6
HDL Cholesterol Normal to Low (≥40 mg/dL to <40 mg/dL) | ABILIFY | 4/108 | 3.7
HDL Cholesterol Normal to Low (≥40 mg/dL to <40 mg/dL) | Placebo | 2/67 | 3.0

Weight Gain

Weight gain has been observed with atypical antipsychotic use. Clinical monitoring of weight is recommended.

Adults

In an analysis of 13, placebo-controlled, monotherapy trials, primarily from pooled schizophrenia and bipolar disorder, with a median exposure of 21 to 25 days, the mean change in body weight in ABILIFY-treated patients was +0.3 kg (N=1673) compared to –0.1 kg (N=1100) in placebo-controlled patients. At 24 weeks, the mean change from baseline in body weight in ABILIFY-treated patients was –1.5 kg (n=73) compared to –0.2 kg (n=46) in placebo-treated patients.

In the trials adding ABILIFY to antidepressants, patients first received 8 weeks of antidepressant treatment followed by 6 weeks of adjunctive ABILIFY or placebo in addition to their ongoing antidepressant treatment. The mean change in body weight in patients receiving adjunctive ABILIFY was +1.7 kg (N=347) compared to +0.4 kg (N=330) in patients receiving adjunctive placebo.

Table 12 shows the percentage of adult patients with weight gain ≥7% of body weight by indication.

Table 12: Percentage of Patients from Placebo-Controlled Trials in Adult Patients with Weight Gain ≥7% of Body Weight
 | Indication | Treatment Arm | N | Patients n (%)
Weight gain ≥7% of body weight | Schizophrenia [4 to 6 weeks duration] | ABILIFY | 852 | 69 (8.1)
Weight gain ≥7% of body weight | Schizophrenia [4 to 6 weeks duration] | Placebo | 379 | 12 (3.2)
Weight gain ≥7% of body weight | Bipolar Mania [3 weeks duration] | ABILIFY | 719 | 16 (2.2)
Weight gain ≥7% of body weight | Bipolar Mania [3 weeks duration] | Placebo | 598 | 16 (2.7)
Weight gain ≥7% of body weight | Major Depressive Disorder (Adjunctive Therapy) [6 weeks duration.] | ABILIFY | 347 | 18 (5.2)
Weight gain ≥7% of body weight | Major Depressive Disorder (Adjunctive Therapy) [6 weeks duration.] | Placebo | 330 | 2 (0.6)

Pediatric Patients and Adolescents

In an analysis of two placebo-controlled trials in adolescents with schizophrenia (13 to 17 years) and pediatric patients with bipolar disorder (10 to 17 years) with median exposure of 42 to 43 days, the mean change in body weight in ABILIFY-treated patients was +1.6 kg (N=381) compared to +0.3 kg (N=187) in placebo-treated patients. At 24 weeks, the mean change from baseline in body weight in ABILIFY-treated patients was +5.8 kg (n=62) compared to +1.4 kg (n=13) in placebo-treated patients.

In two, short-term, placebo-controlled trials in patients (6 to 17 years) with irritability associated with autistic disorder with median exposure of 56 days, the mean change in body weight in ABILIFY-treated patients was +1.6 kg (n=209) compared to +0.4 kg (n=98) in placebo-treated patients.

In two, short-term, placebo-controlled trials in patients (6 to 18 years) with Tourette's Disorder with median exposure of 57 days, the mean change in body weight in ABILIFY-treated patients was +1.5 kg (n=105) compared to +0.4 kg (n=66) in placebo-treated patients.

Table 13 shows the percentage of pediatric and adolescent patients with weight gain ≥7% of body weight by indication.

Table 13: Percentage of Patients from Placebo-Controlled Monotherapy Trials in Pediatric and Adolescent Patients with Weight Gain ≥7% of Body Weight
 | Indication | Treatment Arm | N | Patients n (%)
Weight gain ≥7% of body weight | Pooled Schizophrenia and Bipolar Mania [4 to 6 weeks duration] | ABILIFY | 381 | 20 (5.2)
Weight gain ≥7% of body weight | Pooled Schizophrenia and Bipolar Mania [4 to 6 weeks duration] | Placebo | 187 | 3 (1.6)
Weight gain ≥7% of body weight | Irritability Associated with Autistic Disorder [8 weeks duration] | ABILIFY | 209 | 55 (26.3)
Weight gain ≥7% of body weight | Irritability Associated with Autistic Disorder [8 weeks duration] | Placebo | 98 | 7 (7.1)
Weight gain ≥7% of body weight | Tourette's Disorder [8 to 10 weeks duration.] | ABILIFY | 105 | 21 (20.0)
Weight gain ≥7% of body weight | Tourette's Disorder [8 to 10 weeks duration.] | Placebo | 66 | 5 (7.6)

In an open-label trial that enrolled patients from the two placebo-controlled trials of adolescents with schizophrenia (13 to 17 years) and pediatric patients with bipolar disorder (10 to 17 years), 73.2% of patients (238/325) completed 26 weeks of therapy with ABILIFY. After 26 weeks, 32.8% of patients gained ≥7% of their body weight, not adjusted for normal growth. To adjust for normal growth, z-scores were derived (measured in standard deviations [SD]), which normalize for the natural growth of pediatric patients and adolescents by comparisons to age- and gender-matched population standards. A z-score change <0.5 SD is considered not clinically significant. After 26 weeks, the mean change in z-score was 0.09 SD.

In an open-label trial that enrolled patients from two short-term, placebo-controlled trials, patients (6 to 17 years) with irritability associated with autistic disorder, as well as de novo patients, 60.3% (199/330) completed one year of therapy with ABILIFY. The mean change in weight z-score was 0.26 SDs for patients receiving >9 months of treatment.

When treating pediatric patients for any indication, weight gain should be monitored and assessed against that expected for normal growth.

5.7 Pathological Gambling and Other Compulsive Behaviors

Postmarketing case reports suggest that patients can experience intense urges, particularly for gambling, and the inability to control these urges while taking aripiprazole. Other compulsive urges, reported less frequently, include sexual urges, shopping, eating or binge eating, and other impulsive or compulsive behaviors. Because patients may not recognize these behaviors as abnormal, it is important for prescribers to ask patients or their caregivers specifically about the development of new or intense gambling urges, compulsive sexual urges, compulsive shopping, binge or compulsive eating, or other urges while being treated with aripiprazole. It should be noted that impulse-control symptoms can be associated with the underlying disorder. In some cases, although not all, urges were reported to have stopped when the dose was reduced, or the medication was discontinued. Compulsive behaviors may result in harm to the patient and others if not recognized. Consider dose reduction or stopping the medication if a patient develops such urges.

5.8 Orthostatic Hypotension

ABILIFY may cause orthostatic hypotension, perhaps due to its alpha1-adrenergic receptor antagonism. The incidence of orthostatic hypotension-associated events from short-term, placebo-controlled trials of adult patients on oral ABILIFY (n=2,467) included (ABILIFY incidence, placebo incidence) orthostatic hypotension (1%, 0.3%), postural dizziness (0.5%, 0.3%), and syncope (0.5%, 0.4%); of pediatric patients 6 to 18 years of age (n=732) on oral ABILIFY included orthostatic hypotension (0.5%, 0%), postural dizziness (0.4%, 0%), and syncope (0.2%, 0%) [see Adverse Reactions (6.1)].

The incidence of a significant orthostatic change in blood pressure (defined as a decrease in systolic blood pressure ≥20 mmHg accompanied by an increase in heart rate ≥25 bpm when comparing standing to supine values) for ABILIFY was not meaningfully different from placebo (ABILIFY incidence, placebo incidence): in adult oral ABILIFY-treated patients (4%, 2%), or in pediatric oral ABILIFY-treated patients aged 6 to 18 years (0.4%, 1%).

ABILIFY should be used with caution in patients with known cardiovascular disease (history of myocardial infarction or ischemic heart disease, heart failure or conduction abnormalities), cerebrovascular disease, or conditions which would predispose patients to hypotension (dehydration, hypovolemia, and treatment with antihypertensive medications) [see Drug Interactions (7.1)].

5.9 Falls

Antipsychotics, including ABILIFY, may cause somnolence, postural hypotension, motor and sensory instability, which may lead to falls and, consequently, fractures or other injuries. For patients with diseases, conditions, or medications that could exacerbate these effects, complete fall risk assessments when initiating antipsychotic treatment and recurrently for patients on long-term antipsychotic therapy.

5.10 Leukopenia, Neutropenia, and Agranulocytosis

In clinical trials and/or postmarketing experience, events of leukopenia and neutropenia have been reported temporally related to antipsychotic agents, including ABILIFY. Agranulocytosis has also been reported.

Possible risk factors for leukopenia/neutropenia include pre-existing low white blood cell count (WBC)/absolute neutrophil count (ANC) and history of drug-induced leukopenia/neutropenia. In patients with a history of a clinically significant low WBC/ANC or drug-induced leukopenia/neutropenia, perform a complete blood count (CBC) frequently during the first few months of therapy. In such patients, consider discontinuation of ABILIFY at the first sign of a clinically significant decline in WBC in the absence of other causative factors.

Monitor patients with clinically significant neutropenia for fever or other symptoms or signs of infection and treat promptly if such symptoms or signs occur. Discontinue ABILIFY in patients with severe neutropenia (absolute neutrophil count <1,000/mm^3) and follow their WBC counts until recovery.

5.11 Seizures/Convulsions

In short-term, placebo-controlled trials, patients with a history of seizures excluded seizures/convulsions occurred in 0.1% (3/2,467) of undiagnosed adult patients treated with oral ABILIFY and in 0.1% (1/732) of pediatric patients (6 to 18 years).

As with other antipsychotic drugs, ABILIFY should be used cautiously in patients with a history of seizures or with conditions that lower the seizure threshold. Conditions that lower the seizure threshold may be more prevalent in a population of 65 years or older.

5.12 Potential for Cognitive and Motor Impairment

ABILIFY, like other antipsychotics, may have the potential to impair judgment, thinking, or motor skills. For example, in short-term, placebo-controlled trials, somnolence (including sedation) was reported as follows (ABILIFY incidence, placebo incidence): in adult patients (n=2,467) treated with oral ABILIFY (11%, 6%) and in pediatric patients ages 6 to 17 years (n=611; 24%, 6%). Somnolence (including sedation) led to discontinuation in 0.3% (8/2,467) of adult patients and 3% (20/732) of pediatric patients (6 to 18 years) on oral ABILIFY in short-term, placebo-controlled trials.

Despite the relatively modest increased incidence of these events compared to placebo, patients should be cautioned about operating hazardous machinery, including automobiles, until they are reasonably certain that therapy with ABILIFY does not affect them adversely.

5.13 Body Temperature Regulation

Disruption of the body's ability to reduce core body temperature has been attributed to antipsychotic agents. Appropriate care is advised when prescribing ABILIFY for patients who will be experiencing conditions which may contribute to an elevation in core body temperature, (e.g., exercising strenuously, exposure to extreme heat, receiving concomitant medication with anticholinergic activity, or being subject to dehydration) [see Adverse Reactions (6.2)].

5.14 Suicide

The possibility of a suicide attempt is inherent in psychotic illnesses, bipolar disorder, and major depressive disorder, and close supervision of high-risk patients should accompany drug therapy. Prescriptions for ABILIFY should be written for the smallest quantity consistent with good patient management in order to reduce the risk of overdose [see Adverse Reactions (6.1, 6.2)].

5.15 Dysphagia

Esophageal dysmotility and aspiration have been associated with antipsychotic drug use, including ABILIFY. Aspiration pneumonia is a common cause of morbidity and mortality in elderly patients, in particular those with advanced Alzheimer's dementia. ABILIFY and other antipsychotic drugs should be used cautiously in patients at risk for aspiration pneumonia [see Warnings and Precautions (5.1) and Adverse Reactions (6.2)].

6 ADVERSE REACTIONS

The following adverse reactions are discussed in more detail in other sections of the labeling:

- Increased Mortality in Elderly Patients with Dementia-Related Psychosis [see Boxed Warning and Warnings and Precautions (5.1)]
- Cerebrovascular Adverse Events, Including Stroke [see Warnings and Precautions (5.2)]
- Suicidal Thoughts and Behaviors in Children, Adolescents, and Young Adults [see Boxed Warning and Warnings and Precautions (5.3)]
- Neuroleptic Malignant Syndrome (NMS) [see Warnings and Precautions (5.4)]
- Tardive Dyskinesia [see Warnings and Precautions (5.5)]
- Metabolic Changes [see Warnings and Precautions (5.6)]
- Pathological Gambling and Other Compulsive Behaviors [see Warnings and Precautions (5.7)]
- Orthostatic Hypotension [see Warnings and Precautions (5.8)]
- Falls [see Warnings and Precautions (5.9)]
- Leukopenia, Neutropenia, and Agranulocytosis [see Warnings and Precautions (5.10)]
- Seizures/Convulsions [see Warnings and Precautions (5.11)]
- Potential for Cognitive and Motor Impairment [see Warnings and Precautions (5.12)]
- Body Temperature Regulation [see Warnings and Precautions (5.13)]
- Suicide [see Warnings and Precautions (5.14)]
- Dysphagia [see Warnings and Precautions (5.15)]

6.1 Clinical Trials Experience

Because clinical trials are conducted under widely varying conditions, adverse reaction rates observed in the clinical trials of a drug cannot be directly compared to rates in the clinical trials of another drug and may not reflect the rates observed in practice.

The most common adverse reactions in adult patients in clinical trials (≥10%) were nausea, vomiting, constipation, headache, dizziness, akathisia, anxiety, insomnia, and restlessness.

The most common adverse reactions in the pediatric clinical trials (≥10%) were somnolence, headache, vomiting, extrapyramidal disorder, fatigue, increased appetite, insomnia, nausea, nasopharyngitis, and weight increased.

ABILIFY has been evaluated for safety in 13,543 adult patients who participated in multiple-dose, clinical trials in schizophrenia, bipolar disorder, major depressive disorder, dementia of the Alzheimer's type, Parkinson's disease, and alcoholism, and who had approximately 7,619 patient-years of exposure to oral ABILIFY and 749 patients with exposure to aripiprazole injection. A total of 3,390 patients were treated with oral ABILIFY for at least 180 days and 1,933 patients treated with oral ABILIFY had at least one year of exposure.

ABILIFY has been evaluated for safety in 1,686 pediatric patients (6 to 18 years) who participated in multiple-dose, clinical trials in schizophrenia, bipolar mania, autistic disorder, or Tourette's Disorder and who had approximately 1,342 patient-years of exposure to oral ABILIFY. A total of 959 pediatric patients were treated with oral ABILIFY for at least 180 days and 556 pediatric patients treated with oral ABILIFY had at least one year of exposure.

The conditions and duration of treatment with ABILIFY (monotherapy and adjunctive therapy with antidepressants or mood stabilizers) included (in overlapping categories) double-blind, comparative and noncomparative open-label studies, inpatient and outpatient studies, fixed- and flexible-dose studies, and short- and longer-term exposure.

Adult Patients with Schizophrenia

The following findings are based on a pool of five placebo-controlled trials (four 4-week and one 6-week) in which oral ABILIFY was administered in doses ranging from 2 to 30 mg/day.

Commonly Observed Adverse Reactions

The only commonly observed adverse reaction associated with the use of ABILIFY in patients with schizophrenia (incidence of 5% or greater and ABILIFY incidence at least twice that for placebo) was akathisia (ABILIFY 8%; placebo 4%).

Adult Patients with Bipolar Mania

Monotherapy

The following findings are based on a pool of 3-week, placebo-controlled, bipolar mania trials in which oral ABILIFY was administered at doses of 15 or 30 mg/day.

Commonly Observed Adverse Reactions

Commonly observed adverse reactions associated with the use of ABILIFY in patients with bipolar mania (incidence of 5% or greater and ABILIFY incidence at least twice that for placebo) are shown in Table 14.

Table 14: Commonly Observed Adverse Reactions in Short-Term, Placebo-Controlled Trials of Adult Patients with Bipolar Mania Treated with ABILIFY Monotherapy
Preferred Term | Percentage of Patients Reporting Reaction
Preferred Term | ABILIFY (n=917) | Placebo (n=753)
Akathisia | 13 | 4
Sedation | 8 | 3
Restlessness | 6 | 3
Tremor | 6 | 3
Extrapyramidal Disorder | 5 | 2

Less Common Adverse Reactions in Adults

Table 15 enumerates the pooled incidence, rounded to the nearest percent, of adverse reactions that occurred during acute therapy (up to 6 weeks in schizophrenia and up to 3 weeks in bipolar mania), including only those reactions that occurred in 2% or more of patients treated with ABILIFY (doses ≥2 mg/day) and for which the incidence in patients treated with ABILIFY was greater than the incidence in patients treated with placebo in the combined dataset.

Table 15: Adverse Reactions in Short-Term, Placebo-Controlled Trials in Adult Patients Treated with ABILIFY
Preferred Term | Percentage of Patients Reporting Reaction [Adverse reactions reported by at least 2% of patients treated with ABILIFY, except adverse reactions which had an incidence equal to or less than placebo.]
Preferred Term | ABILIFY (n=1,843) | Placebo (n=1,166)
Eye Disorders
Blurred Vision | 3 | 1
Gastrointestinal Disorders
Nausea | 15 | 11
Constipation | 11 | 7
Vomiting | 11 | 6
Dyspepsia | 9 | 7
Dry Mouth | 5 | 4
Toothache | 4 | 3
Abdominal Discomfort | 3 | 2
Stomach Discomfort | 3 | 2
General Disorders and Administration Site Conditions
Fatigue | 6 | 4
Pain | 3 | 2
Musculoskeletal and Connective Tissue Disorders
Musculoskeletal Stiffness | 4 | 3
Pain in Extremity | 4 | 2
Myalgia | 2 | 1
Muscle Spasms | 2 | 1
Nervous System Disorders
Headache | 27 | 23
Dizziness | 10 | 7
Akathisia | 10 | 4
Sedation | 7 | 4
Extrapyramidal Disorder | 5 | 3
Tremor | 5 | 3
Somnolence | 5 | 3
Psychiatric Disorders
Agitation | 19 | 17
Insomnia | 18 | 13
Anxiety | 17 | 13
Restlessness | 5 | 3
Respiratory, Thoracic, and Mediastinal Disorders
Pharyngolaryngeal Pain | 3 | 2
Cough | 3 | 2

An examination of population subgroups did not reveal any clear evidence of differential adverse reaction incidence on the basis of age, gender, or race.

Adult Patients with Adjunctive Therapy with Bipolar Mania

The following findings are based on a placebo-controlled trial of adult patients with bipolar disorder in which ABILIFY was administered at doses of 15 or 30 mg/day as adjunctive therapy with lithium or valproate.

Adverse Reactions Associated with Discontinuation of Treatment

In a study of patients who were already tolerating either lithium or valproate as monotherapy, discontinuation rates due to adverse reactions were 12% for patients treated with adjunctive ABILIFY compared to 6% for patients treated with adjunctive placebo. The most common adverse drug reactions associated with discontinuation in the adjunctive ABILIFY-treated compared to placebo-treated patients were akathisia (5% and 1%, respectively) and tremor (2% and 1%, respectively).

Commonly Observed Adverse Reactions

The commonly observed adverse reactions associated with adjunctive ABILIFY and lithium or valproate in patients with bipolar mania (incidence of 5% or greater and incidence at least twice that for adjunctive placebo) were: akathisia, insomnia, and extrapyramidal disorder.

Less Common Adverse Reactions in Adult Patients with Adjunctive Therapy in Bipolar Mania

Table 16 enumerates the incidence, rounded to the nearest percent, of adverse reactions that occurred during acute treatment (up to 6 weeks), including only those reactions that occurred in 2% or more of patients treated with adjunctive ABILIFY (doses of 15 or 30 mg/day) and lithium or valproate and for which the incidence in patients treated with this combination was greater than the incidence in patients treated with placebo plus lithium or valproate.

Table 16: Adverse Reactions in a Short-Term, Placebo-Controlled Trial of Adjunctive Therapy in Patients with Bipolar Disorder
Preferred Term | Percentage of Patients Reporting Reaction [Adverse reactions reported by at least 2% of patients treated with ABILIFY, except adverse reactions which had an incidence equal to or less than placebo.]
Preferred Term | ABILIFY + Li or Val [Lithium or Valproate] (n=253) | Placebo + Li or Val (n=130)
Gastrointestinal Disorders
Nausea | 8 | 5
Vomiting | 4 | 0
Salivary Hypersecretion | 4 | 2
Dry Mouth | 2 | 1
Infections and Infestations
Nasopharyngitis | 3 | 2
Investigations
Weight Increased | 2 | 1
Nervous System Disorders
Akathisia | 19 | 5
Tremor | 9 | 6
Extrapyramidal Disorder | 5 | 1
Dizziness | 4 | 1
Sedation | 4 | 2
Psychiatric Disorders
Insomnia | 8 | 4
Anxiety | 4 | 1
Restlessness | 2 | 1

Pediatric Patients (13 to 17 years) with Schizophrenia

The following findings are based on one 6-week, placebo-controlled trial in which oral ABILIFY was administered in doses ranging from 2 to 30 mg/day.

Adverse Reactions Associated with Discontinuation of Treatment

The incidence of discontinuation due to adverse reactions between pediatric patients (13 to 17 years) treated with ABILIFY and treated with placebo was 5% and 2%, respectively.

Commonly Observed Adverse Reactions

Commonly observed adverse reactions associated with the use of ABILIFY in adolescent patients with schizophrenia (incidence of 5% or greater and ABILIFY incidence at least twice that for placebo) were extrapyramidal disorder, somnolence, and tremor.

Pediatric Patients (10 to 17 years) with Bipolar Mania

The following findings are based on one 4-week, placebo-controlled trial in which oral ABILIFY was administered in doses of 10 or 30 mg/day.

Adverse Reactions Associated with Discontinuation of Treatment

The incidence of discontinuation due to adverse reactions between pediatric patients (10 to 17 years) treated with ABILIFY and treated with placebo was 7% and 2%, respectively.

Commonly Observed Adverse Reactions

Commonly observed adverse reactions associated with the use of ABILIFY in pediatric patients with bipolar mania (incidence of 5% or greater and ABILIFY incidence at least twice that for placebo) are shown in Table 17.

Table 17: Commonly Observed Adverse Reactions in Short-Term, Placebo-Controlled Trials of Pediatric Patients (10 to 17 years) with Bipolar Mania Treated with ABILIFY
Preferred Term | Percentage of Patients Reporting Reaction
Preferred Term | ABILIFY (n=197) | Placebo (n=97)
Somnolence | 23 | 3
Extrapyramidal Disorder | 20 | 3
Fatigue | 11 | 4
Nausea | 11 | 4
Akathisia | 10 | 2
Blurred Vision | 8 | 0
Salivary Hypersecretion | 6 | 0
Dizziness | 5 | 1

Pediatric Patients (6 to 17 years) with Autistic Disorder

The following findings are based on two 8-week, placebo-controlled trials in which oral ABILIFY was administered in doses of 2 to 15 mg/day.

Adverse Reactions Associated with Discontinuation of Treatment

The incidence of discontinuation due to adverse reactions between pediatric patients (6 to 17 years) treated with ABILIFY and treated with placebo was 10% and 8%, respectively.

Commonly Observed Adverse Reactions

Commonly observed adverse reactions associated with the use of ABILIFY in pediatric patients with autistic disorder (incidence of 5% or greater and ABILIFY incidence at least twice that for placebo) are shown in Table 18.

Table 18: Commonly Observed Adverse Reactions in Short-Term, Placebo-Controlled Trials of Pediatric Patients (6 to 17 years) with Autistic Disorder Treated with ABILIFY
Preferred Term | Percentage of Patients Reporting Reaction
Preferred Term | ABILIFY (n=212) | Placebo (n=101)
Sedation | 21 | 4
Fatigue | 17 | 2
Vomiting | 14 | 7
Somnolence | 10 | 4
Tremor | 10 | 0
Pyrexia | 9 | 1
Drooling | 9 | 0
Decreased Appetite | 7 | 2
Salivary Hypersecretion | 6 | 1
Extrapyramidal Disorder | 6 | 0
Lethargy | 5 | 0

Pediatric Patients (6 to 18 years) with Tourette's Disorder

The following findings are based on one 8-week and one 10-week, placebo-controlled trials in which oral ABILIFY was administered in doses of 2 to 20 mg/day.

Adverse Reactions Associated with Discontinuation of Treatment

The incidence of discontinuation due to adverse reactions between pediatric patients (6 to 18 years) treated with ABILIFY and treated with placebo was 7% and 1%, respectively.

Commonly Observed Adverse Reactions

Commonly observed adverse reactions associated with the use of ABILIFY in pediatric patients with Tourette's Disorder (incidence of 5% or greater and ABILIFY incidence at least twice that for placebo) are shown in Table 19.

Table 19: Commonly Observed Adverse Reactions in Short-Term, Placebo-Controlled Trials of Pediatric Patients (6 to 18 years) with Tourette's Disorder Treated with ABILIFY
Preferred Term | Percentage of Patients Reporting Reaction
Preferred Term | ABILIFY (n=121) | Placebo (n=72)
Sedation | 13 | 6
Somnolence | 13 | 1
Nausea | 11 | 4
Headache | 10 | 3
Nasopharyngitis | 9 | 0
Fatigue | 8 | 0
Increased Appetite | 7 | 1

Less Common Adverse Reactions in Pediatric Patients (6 to 18 years) with Schizophrenia, Bipolar Mania, Autistic Disorder, or Tourette's Disorder

Table 20 enumerates the pooled incidence, rounded to the nearest percent, of adverse reactions that occurred during acute therapy (up to 6 weeks in schizophrenia, up to 4 weeks in bipolar mania, up to 8 weeks in autistic disorder, and up to 10 weeks in Tourette's Disorder), including only those reactions that occurred in 2% or more of pediatric patients treated with ABILIFY (doses ≥2 mg/day) and for which the incidence in patients treated with ABILIFY was greater than the incidence in patients treated with placebo.

Table 20: Adverse Reactions in Short-Term, Placebo-Controlled Trials of Pediatric Patients (6 to 18 years) Treated with ABILIFY
Preferred Term | Percentage of Patients Reporting Reaction [Adverse reactions reported by at least 2% of pediatric patients treated with ABILIFY, except adverse reactions which had an incidence equal to or less than placebo.]
Preferred Term | ABILIFY (n=732) | Placebo (n=370)
Eye Disorders
Blurred Vision | 3 | 0
Gastrointestinal Disorders
Abdominal Discomfort | 2 | 1
Vomiting | 8 | 7
Nausea | 8 | 4
Diarrhea | 4 | 3
Salivary Hypersecretion | 4 | 1
Abdominal Pain Upper | 3 | 2
Constipation | 2 | 2
General Disorders and Administration Site Conditions
Fatigue | 10 | 2
Pyrexia | 4 | 1
Irritability | 2 | 1
Asthenia | 2 | 1
Infections and Infestations
Nasopharyngitis | 6 | 3
Investigations
Weight Increased | 3 | 1
Metabolism and Nutrition Disorders
Increased Appetite | 7 | 3
Decreased Appetite | 5 | 4
Musculoskeletal and Connective Tissue Disorders
Musculoskeletal Stiffness | 2 | 1
Muscle Rigidity | 2 | 1
Nervous System Disorders
Somnolence | 16 | 4
Headache | 12 | 10
Sedation | 9 | 2
Tremor | 9 | 1
Extrapyramidal Disorder | 6 | 1
Akathisia | 6 | 4
Drooling | 3 | 0
Lethargy | 3 | 0
Dizziness | 3 | 2
Dystonia | 2 | 1
Respiratory, Thoracic, and Mediastinal Disorders
Epistaxis | 2 | 1
Skin and Subcutaneous Tissue Disorders
Rash | 2 | 1

Adult Patients Receiving ABILIFY as Adjunctive Treatment of Major Depressive Disorder

The following findings are based on a pool of two placebo-controlled trials of patients with major depressive disorder in which ABILIFY was administered at doses of 2 to 20 mg as adjunctive treatment to continued antidepressant therapy.

Adverse Reactions Associated with Discontinuation of Treatment

The incidence of discontinuation due to adverse reactions was 6% for patients treated with adjunctive ABILIFY and 2% for patients treated with adjunctive placebo.

Commonly Observed Adverse Reactions

The commonly observed adverse reactions associated with the use of adjunctive ABILIFY in patients with major depressive disorder (incidence of 5% or greater and ABILIFY incidence at least twice that for placebo) were: akathisia, restlessness, insomnia, constipation, fatigue, and blurred vision.

Less Common Adverse Reactions in Adult Patients with Major Depressive Disorder

Table 21 enumerates the pooled incidence, rounded to the nearest percent, of adverse reactions that occurred during acute therapy (up to 6 weeks), including only those adverse reactions that occurred in 2% or more of patients treated with adjunctive ABILIFY (doses ≥2 mg/day) and for which the incidence in patients treated with adjunctive ABILIFY was greater than the incidence in patients treated with adjunctive placebo in the combined dataset.

Table 21: Adverse Reactions in Short-Term, Placebo-Controlled Adjunctive Trials in Patients with Major Depressive Disorder
Preferred Term | Percentage of Patients Reporting Reaction [Adverse reactions reported by at least 2% of patients treated with adjunctive ABILIFY, except adverse reactions which had an incidence equal to or less than placebo.]
Preferred Term | ABILIFY + ADT [Antidepressant Therapy] (n=371) | Placebo + ADT (n=366)
Eye Disorders
Blurred Vision | 6 | 1
Gastrointestinal Disorders
Constipation | 5 | 2
General Disorders and Administration Site Conditions
Fatigue | 8 | 4
Feeling Jittery | 3 | 1
Infections and Infestations
Upper Respiratory Tract Infection | 6 | 4
Investigations
Weight Increased | 3 | 2
Metabolism and Nutrition Disorders
Increased Appetite | 3 | 2
Musculoskeletal and Connective Tissue Disorders
Arthralgia | 4 | 3
Myalgia | 3 | 1
Nervous System Disorders
Akathisia | 25 | 4
Somnolence | 6 | 4
Tremor | 5 | 4
Sedation | 4 | 2
Dizziness | 4 | 2
Disturbance in Attention | 3 | 1
Extrapyramidal Disorder | 2 | 0
Psychiatric Disorders
Restlessness | 12 | 2
Insomnia | 8 | 2

Dose-Related Adverse Reactions

Schizophrenia

Dose response relationships for the incidence of treatment-emergent adverse events were evaluated from four trials in adult patients with schizophrenia comparing various fixed doses (2, 5, 10, 15, 20, and 30 mg/day) of oral ABILIFY to placebo. This analysis, stratified by study, indicated that the only adverse reaction to have a possible dose response relationship, and then most prominent only with 30 mg, was somnolence [including sedation]; (incidences were placebo, 7.1%; 10 mg, 8.5%; 15 mg, 8.7%; 20 mg, 7.5%; 30 mg, 12.6%).

In the study of pediatric patients (13 to 17 years of age) with schizophrenia, three common adverse reactions appeared to have a possible dose response relationship: extrapyramidal disorder (incidences were placebo, 5.0%; 10 mg, 13.0%; 30 mg, 21.6%); somnolence (incidences were placebo, 6.0%; 10 mg, 11.0%; 30 mg, 21.6%); and tremor (incidences were placebo, 2.0%; 10 mg, 2.0%; 30 mg, 11.8%).

Bipolar Mania

In the study of pediatric patients (10 to 17 years of age) with bipolar mania, four common adverse reactions had a possible dose response relationship at 4 weeks; extrapyramidal disorder (incidences were placebo, 3.1%; 10 mg, 12.2%; 30 mg, 27.3%); somnolence (incidences were placebo, 3.1%; 10 mg, 19.4%; 30 mg, 26.3%); akathisia (incidences were placebo, 2.1%; 10 mg, 8.2%; 30 mg, 11.1%); and salivary hypersecretion (incidences were placebo, 0%; 10 mg, 3.1%; 30 mg, 8.1%).

Autistic Disorder

In a study of pediatric patients (6 to 17 years of age) with autistic disorder, one common adverse reaction had a possible dose response relationship: fatigue (incidences were placebo, 0%; 5 mg, 3.8%; 10 mg, 22.0%; 15 mg, 18.5%).

Tourette's Disorder

In a study of pediatric patients (7 to 17 years of age) with Tourette's Disorder, no common adverse reaction(s) had a dose response relationship.

Extrapyramidal Symptoms

Schizophrenia

In short-term, placebo-controlled trials in schizophrenia in adults, the incidence of reported EPS-related events, excluding events related to akathisia, for ABILIFY-treated patients was 13% vs. 12% for placebo; and the incidence of akathisia-related events for ABILIFY-treated patients was 8% vs. 4% for placebo. In the short-term, placebo-controlled trial of schizophrenia in pediatric patients (13 to 17 years), the incidence of reported EPS-related events, excluding events related to akathisia, for ABILIFY-treated patients was 25% vs. 7% for placebo; and the incidence of akathisia-related events for ABILIFY-treated patients was 9% vs. 6% for placebo.

Objectively collected data from those trials was collected for EPS using the Simpson Angus Scale (SAS), for akathisia using the Barnes Akathisia Rating Scale (BARS), and for dyskinesias using the Assessments of Involuntary Movement Scales (AIMS). In the adult schizophrenia trials, the objectively collected data did not show a difference between ABILIFY and placebo, with the exception of the BARS (ABILIFY, 0.08; placebo, –0.05). In the pediatric (13 to 17 years) schizophrenia trial, the objectively collected data did not show a difference between ABILIFY and placebo, with the exception of the SAS (ABILIFY, 0.24; placebo, –0.29).

Similarly, in a long-term (26 week), placebo-controlled trial of schizophrenia in adults, objectively collected data for EPS using the SAS, for akathisia using the BARS, and for dyskinesias using the AIMS did not show a difference between ABILIFY and placebo.

Bipolar Mania

In the short-term, placebo-controlled trials in bipolar mania in adults, the incidence of reported EPS-related events, excluding events related to akathisia, for monotherapy ABILIFY-treated patients was 16% vs. 8% for placebo and the incidence of akathisia-related events for monotherapy ABILIFY-treated patients was 13% vs. 4% for placebo. In the 6-week, placebo-controlled trial in bipolar mania for adjunctive therapy with lithium or valproate, the incidence of reported EPS-related events, excluding events related to akathisia for adjunctive ABILIFY-treated patients was 15% vs. 8% for adjunctive placebo and the incidence of akathisia-related events for adjunctive ABILIFY-treated patients was 19% vs. 5% for adjunctive placebo. In the short-term, placebo-controlled trial in bipolar mania in pediatric (10 to 17 years) patients, the incidence of reported EPS-related events, excluding events related to akathisia, for ABILIFY-treated patients treated with was 26% vs. 5% for placebo and the incidence of akathisia-related events for ABILIFY-treated patients was 10% vs. 2% for placebo.

In the adult bipolar mania trials with monotherapy ABILIFY, the SAS and the BARS showed a significant difference between ABILIFY and placebo (ABILIFY, 0.50; placebo, –0.01 and ABILIFY, 0.21; placebo, –0.05). Changes in the AIMS were similar for the ABILIFY and placebo groups. In the bipolar mania trials with ABILIFY as adjunctive therapy with either lithium or valproate, the SAS and the BARS showed a significant difference between adjunctive ABILIFY and adjunctive placebo (ABILIFY, 0.73; placebo, 0.07 and ABILIFY, 0.30; placebo, 0.11). Changes in the AIMS were similar for adjunctive ABILIFY and adjunctive placebo. In the pediatric (10 to 17 years), short-term, bipolar mania trial, the SAS showed a significant difference between ABILIFY and placebo (ABILIFY, 0.90; placebo, −0.05). Changes in the BARS and the AIMS were similar for the ABILIFY and placebo groups.

Major Depressive Disorder

In the short-term, placebo-controlled trials in major depressive disorder, the incidence of reported EPS-related events, excluding events related to akathisia, for adjunctive ABILIFY-treated patients was 8% vs. 5% for adjunctive placebo-treated patients; and the incidence of akathisia-related events for adjunctive ABILIFY-treated patients was 25% vs. 4% for adjunctive placebo-treated patients.

In the major depressive disorder trials, the SAS and the BARS showed a significant difference between adjunctive ABILIFY and adjunctive placebo (ABILIFY, 0.31; placebo, 0.03 and ABILIFY, 0.22; placebo, 0.02). Changes in the AIMS were similar for the adjunctive ABILIFY and adjunctive placebo groups.

Autistic Disorder

In the short-term, placebo-controlled trials in autistic disorder in pediatric patients (6 to 17 years), the incidence of reported EPS-related events, excluding events related to akathisia, for ABILIFY-treated patients was 18% vs. 2% for placebo and the incidence of akathisia-related events for ABILIFY-treated patients was 3% vs. 9% for placebo.

In the pediatric (6 to 17 years) short-term autistic disorder trials, the SAS showed a significant difference between ABILIFY and placebo (ABILIFY, 0.1; placebo, –0.4). Changes in the BARS and the AIMS were similar for the ABILIFY and placebo groups.

Tourette's Disorder

In the short-term, placebo-controlled trials in Tourette's Disorder in pediatric patients (6 to 18 years), the incidence of reported EPS-related events, excluding events related to akathisia, for ABILIFY-treated patients was 7% vs. 6% for placebo and the incidence of akathisia-related events for ABILIFY-treated patients was 4% vs. 6% for placebo.

In the pediatric (6 to 18 years) short-term Tourette's Disorder trials, changes in the SAS, BARS and AIMS were not clinically meaningfully different for ABILIFY and placebo.

Dystonia

Symptoms of dystonia, prolonged abnormal contractions of muscle groups, may occur in susceptible individuals during the first few days of treatment. Dystonic symptoms include spasm of the neck muscles, sometimes progressing to tightness of the throat, swallowing difficulty, difficulty breathing, and/or protrusion of the tongue. While these symptoms can occur at low doses, they occur more frequently and with greater severity with high potency and at higher doses of first generation antipsychotic drugs. An elevated risk of acute dystonia is observed in males and younger age groups.

Additional Findings Observed in Clinical Trials

Adverse Reactions in Long-Term, Double-Blind, Placebo-Controlled Trials

The adverse reactions reported in a 26-week, double-blind trial comparing oral ABILIFY and placebo in patients with schizophrenia were generally consistent with those reported in the short-term, placebo-controlled trials, except for a higher incidence of tremor [8% (12/153) for ABILIFY vs. 2% (3/153) for placebo]. In this study, the majority of the cases of tremor were of mild intensity (8/12 mild and 4/12 moderate), occurred early in therapy (9/12 ≤49 days), and were of limited duration (7/12 ≤10 days). Tremor infrequently led to discontinuation (<1%) of ABILIFY. In addition, in a long-term (52 weeks), active-controlled study, the incidence of tremor was 5% (40/859) for ABILIFY. A similar profile was observed in a long-term monotherapy study and a long-term adjunctive study with lithium and valproate in bipolar disorder.

Other Adverse Reactions Observed During the Premarketing Evaluation of ABILIFY

The following listing does not include reactions: 1) already listed in previous tables or elsewhere in labeling, 2) for which a drug cause was remote, 3) which were so general as to be uninformative, 4) which were not considered to have significant clinical implications, or 5) which occurred at a rate equal to or less than placebo.

Reactions are categorized by body system according to the following definitions: frequent adverse reactions are those occurring in at least 1/100 patients; infrequent adverse reactions are those occurring in 1/100 to 1/1,000 patients; rare reactions are those occurring in fewer than 1/1,000 patients:

Adults

- Blood and Lymphatic System Disorders: rare – thrombocytopenia
- Cardiac Disorders: infrequent – bradycardia, palpitations, rare – atrial flutter, cardio-respiratory arrest, atrioventricular block, atrial fibrillation, angina pectoris, myocardial ischemia, myocardial infarction, cardiopulmonary failure
- Eye Disorders: infrequent – photophobia; rare – diplopia
- Gastrointestinal Disorders: infrequent – gastroesophageal reflux disease
- General Disorders and Administration Site Conditions: frequent – asthenia; infrequent – peripheral edema, chest pain; rare – face edema
- Hepatobiliary Disorders: rare – hepatitis, jaundice
- Immune System Disorders: rare – hypersensitivity
- Injury, Poisoning, and Procedural Complications: infrequent – fall; rare – heat stroke
- Investigations: frequent – blood prolactin decreased, weight decreased, infrequent – hepatic enzyme increased, blood glucose increased, blood lactate dehydrogenase increased, gamma glutamyl transferase increased; rare – blood prolactin increased, blood urea increased, blood creatinine increased, blood bilirubin increased, electrocardiogram QT prolonged, glycosylated hemoglobin increased
- Metabolism and Nutrition Disorders: frequent – anorexia; rare – hypokalemia, hyponatremia, hypoglycemia
- Musculoskeletal and Connective Tissue Disorders: infrequent – muscular weakness, muscle tightness; rare – rhabdomyolysis, mobility decreased
- Nervous System Disorders: infrequent – parkinsonism, memory impairment, cogwheel rigidity, hypokinesia, bradykinesia; rare – akinesia, myoclonus, coordination abnormal, speech disorder, Grand Mal convulsion; <1/10,000 patients – choreoathetosis
- Psychiatric Disorders: infrequent – aggression, loss of libido, delirium; rare – libido increased, anorgasmia, tic, homicidal ideation, catatonia, sleepwalking
- Renal and Urinary Disorders: rare – urinary retention, nocturia
- Reproductive System and Breast Disorders: infrequent – erectile dysfunction; rare – gynecomastia, menstruation irregular, amenorrhea, breast pain, priapism
- Respiratory, Thoracic, and Mediastinal Disorders: infrequent – nasal congestion, dyspnea
- Skin and Subcutaneous Tissue Disorders: infrequent – rash, hyperhidrosis, pruritus, photosensitivity reaction, alopecia; rare – urticaria
- Vascular Disorders: infrequent – hypotension, hypertension

Pediatric Patients

Most adverse events observed in the pooled database of 1,686 pediatric patients, aged 6 to 18 years, were also observed in the adult population. Additional adverse reactions observed in the pediatric population are listed below.

- Eye Disorders: infrequent – oculogyric crisis
- Gastrointestinal Disorders: infrequent – tongue dry, tongue spasm
- Investigations: frequent – blood insulin increased
- Nervous System Disorders: infrequent – sleep talking
- Renal and Urinary Disorders: frequent – enuresis
- Skin and Subcutaneous Tissue Disorders: infrequent – hirsutism

6.2 Postmarketing Experience

The following adverse reactions have been identified during postapproval use of ABILIFY. Because these reactions are reported voluntarily from a population of uncertain size, it is not always possible to reliably estimate their frequency or establish a causal relationship to drug exposure: occurrences of allergic reaction (anaphylactic reaction, angioedema, laryngospasm, pruritus/urticaria, or oropharyngeal spasm), blood glucose fluctuation, drug reaction with eosinophilia and systemic symptoms (DRESS), hiccups, oculogyric crisis, pathological gambling, and fecal incontinence.

7 DRUG INTERACTIONS

7.1 Drugs Having Clinically Important Interactions with ABILIFY

Table 22: Clinically Important Drug Interactions with ABILIFY:
Concomitant Drug Name or Drug Class | Clinical Rationale | Clinical Recommendation
Strong CYP3A4 Inhibitors (e.g., itraconazole, clarithromycin) or strong CYP2D6 inhibitors (e.g., quinidine, fluoxetine, paroxetine) | Concomitant use of ABILIFY with strong CYP3A4 or CYP2D6 inhibitors increased the exposure of aripiprazole compared to the use of ABILIFY alone [see Clinical Pharmacology (12.3)]. | Reduce the ABILIFY dosage when administered concomitantly with a strong CYP3A4 inhibitor or a strong CYP2D6 inhibitor [see Dosage and Administration (2.6)].
Strong CYP3A4 Inducers (e.g., carbamazepine, rifampin) | Concomitant use of ABILIFY and carbamazepine decreased the exposure of aripiprazole compared to the use of ABILIFY alone [see Clinical Pharmacology (12.3)]. | Increase the ABILIFY dosage when administered concomitantly with a strong CYP3A4 inducer [see Dosage and Administration (2.6)].
Antihypertensive Drugs | Due to its alpha1-adrenergic antagonism, aripiprazole has the potential to enhance the effect of certain antihypertensive agents. | Monitor blood pressure and adjust dose accordingly [see Warnings and Precautions (5.8)].
Benzodiazepines (e.g., lorazepam) | The intensity of sedation was greater with the combination of oral aripiprazole and lorazepam as compared to that observed with aripiprazole alone. The orthostatic hypotension observed was greater with the combination as compared to that observed with lorazepam alone [see Warnings and Precautions (5.8)]. | Monitor sedation and blood pressure. Adjust dose accordingly.

7.2 Drugs Having No Clinically Important Interactions with ABILIFY

Based on pharmacokinetic studies, no dosage adjustment of ABILIFY is required when administered concomitantly with famotidine, valproate, lithium, and lorazepam.

In addition, no dosage adjustment is necessary for substrates of CYP2D6 (e.g., dextromethorphan, fluoxetine, paroxetine, or venlafaxine), CYP2C9 (e.g., warfarin), CYP2C19 (e.g., omeprazole, warfarin, escitalopram), or CYP3A4 (e.g., dextromethorphan) when coadministered with ABILIFY. Additionally, no dosage adjustment is necessary for valproate, lithium, lamotrigine, lorazepam, or sertraline when coadministered with ABILIFY [see Clinical Pharmacology (12.3)].

8 USE IN SPECIFIC POPULATIONS

8.1 Pregnancy

Pregnancy Exposure Registry

There is a pregnancy exposure registry that monitors pregnancy outcomes in women exposed to atypical antipsychotics, including ABILIFY, during pregnancy. Healthcare providers are encouraged to register patients by contacting the National Pregnancy Registry for Atypical Antipsychotics at 1-866-961-2388 or visit http://womensmentalhealth.org/clinical-and-research-programs/pregnancyregistry/.

Risk Summary

Neonates exposed to antipsychotic drugs, including ABILIFY, during the third trimester of pregnancy are at risk for extrapyramidal and/or withdrawal symptoms following delivery (see Clinical Considerations). Overall available data from published epidemiologic studies of pregnant women exposed to aripiprazole have not established a drug-associated risk of major birth defects, miscarriage, or adverse maternal outcomes (see Data). There are risks to the mother associated with untreated schizophrenia, bipolar I disorder, or major depressive disorder, and with exposure to antipsychotics, including ABILIFY, during pregnancy (see Clinical Considerations). Aripiprazole exposure during pregnancy may decrease milk supply in the post-partum period [see Use in Specific Populations (8.2)].

In animal reproduction studies, aripiprazole administration during organogenesis in rats and/or rabbits at doses 10 and 19 times, respectively, the maximum recommended human dose (MRHD) of 30 mg/day based on mg/m^2 body surface area, produced fetal death, decreased fetal weight, undescended testicles, delayed skeletal ossification, skeletal abnormalities, and diaphragmatic hernia. Aripiprazole administration during the pre- and post-natal period in rats at doses 10 times the MRHD based on mg/m^2 body surface area, produced prolonged gestation, stillbirths, decreased pup weight, and decreased pup survival (see Data).

The background risk of major birth defects and miscarriage for the indicated population is unknown. All pregnancies have a background risk of birth defect, loss, or other adverse outcomes. In the U.S. general population, the estimated background risk of major birth defects and miscarriage in clinically recognized pregnancies is 2 to 4% and 15 to 20%, respectively.

Clinical Considerations

Disease-associated maternal and/or embryo/fetal risk

There is a risk to the mother from untreated schizophrenia or bipolar I disorder, including increased risk of relapse, hospitalization, and suicide. Schizophrenia and bipolar I disorder are associated with increased adverse perinatal outcomes, including preterm birth. It is not known if this is a direct result of the illness or other comorbid factors.

A prospective, longitudinal study followed 201 pregnant women with a history of major depressive disorder who were euthymic and taking antidepressants at the beginning of pregnancy. The women who discontinued antidepressants during pregnancy were more likely to experience a relapse of major depression than women who continued antidepressants. Consider the risk of untreated depression when discontinuing or changing treatment with antidepressant medication during pregnancy and postpartum.

Fetal/Neonatal Adverse Reactions

Extrapyramidal and/or withdrawal symptoms, including agitation, hypertonia, hypotonia, tremor, somnolence, respiratory distress, and feeding disorder have been reported in neonates who were exposed to antipsychotic drugs (including ABILIFY) during the third trimester of pregnancy. These symptoms have varied in severity. Monitor neonates for extrapyramidal and/or withdrawal symptoms and manage symptoms appropriately. Some neonates recovered within hours or days without specific treatment; others required prolonged hospitalization.

Data

Human Data

Published data from observational studies, birth registries, and case reports on the use of atypical antipsychotics during pregnancy do not report a clear association with antipsychotics and major birth defects. A retrospective study from a Medicaid database of 9,258 women exposed to antipsychotics during pregnancy did not indicate an overall increased risk for major birth defects.

Animal Data

In animal studies, aripiprazole demonstrated developmental toxicity, including possible teratogenic effects in rats and rabbits.

In pregnant rats treated orally with aripiprazole during organogenesis at doses of 3, 10, and 30 mg/kg/day, which are approximately 1, 3 and 10 times the MRHD of 30 mg/day based on mg/m^2 body surface area, a slight prolongation of gestation and delay in fetal development, as evidenced by decreased fetal weight and undescended testes, were observed at 10 times the MRHD. Delayed skeletal ossification was observed at 3 and 10 times the MRHD. Delivered offspring had increased incidences of hepatodiaphragmatic nodules and diaphragmatic hernia were observed at 10 times the MRHD (the other dose groups were not examined for these findings). Postnatally, delayed vaginal opening was seen at 3 and 10 times the MRHD. Impaired reproductive performance (decreased fertility rate, corpora lutea, implants, live fetuses, and increased post-implantation loss, likely mediated through effects on female offspring) were observed at 10 times the MRHD; however, there was no evidence to suggest that these developmental effects were secondary to maternal toxicity.

In pregnant rats injected intravenously with aripiprazole during organogenesis at doses of 3, 9, and 27 mg/kg/day, which are 1, 3, and 9 times the MRHD of 30 mg/day based on mg/m^2 body surface area, decreased fetal weight and delayed skeletal ossification were observed at 9 times the MRHD; this dose also caused maternal toxicity.

In pregnant rabbits treated orally with aripiprazole during organogenesis at doses of 10, 30, and 100 mg/kg/day which are 6, 19, and 65 times the MRHD of 30 mg/day based on mg/m^2 body surface area, decreased maternal food consumption, and increased abortions as well as increased fetal mortality were observed at 65 times the MRHD. Decreased fetal weight and increased incidence of fused sternebrae were observed at 19 and 65 times the MRHD.

In pregnant rabbits injected intravenously with aripiprazole during organogenesis at doses of 3, 10, and 30 mg/kg/day, which are 2, 6, and 19 times the MRHD of 30 mg/day based on mg/m^2 body surface area, decreased fetal weight, increased fetal abnormalities (primarily skeletal), and decreased fetal skeletal ossification were observed at 19 times the MRHD; this dose also caused maternal toxicity. The fetal no-effect dose was 10 mg/kg/day, which is 6 times the MRHD.

In rats treated orally with aripiprazole peri- and postnatally from gestation Day 17 through postpartum Day 21 at doses of 3, 10, and 30 mg/kg/day which are 1, 3, and 10 times the MRHD of 30 mg/day based on mg/m^2 body surface area slight maternal toxicity and slightly prolonged gestation were observed at 10 times the MRHD. An increase in stillbirths and, decreases in pup weight (persisting into adulthood) and survival were also seen at this dose.

In rats injected intravenously with aripiprazole from gestation Day 6 through lactation Day 20 at doses of 3, 8, and 20 mg/kg/day, which are 1, 3, and 6 times the MRHD of 30 mg/day based on mg/m^2 body surface area, increased stillbirths were observed at 3 and 6 times the MRHD; and decreases in early postnatal pup weight and survival were observed at 6 times the MRHD; these doses also caused some maternal toxicity. There were no effects on postnatal behavioral and reproductive development.

8.2 Lactation

Risk Summary

Aripiprazole is present in human breast milk. Based on published case reports and pharmacovigilance reports, aripiprazole exposure during pregnancy and/or the postpartum period may lead to clinically relevant decreases in milk supply which may be reversible with discontinuation of the drug. There are also reports of aripiprazole exposure during pregnancy and no maternal milk supply in the post-partum period. Effects on milk supply may be mediated through decreases in prolactin levels, which have been observed [see Adverse Reactions (6.1)]. Monitor the breastfed infant for dehydration and lack of appropriate weight gain. The developmental and health benefits of breastfeeding should be considered along with the mother's clinical need for ABILIFY and any potential adverse effects on the breastfed infant from ABILIFY or from the underlying maternal condition.

8.4 Pediatric Use

Safety and effectiveness in pediatric patients with major depressive disorder or agitation associated with schizophrenia or bipolar mania have not been established.

The pharmacokinetics of aripiprazole and dehydro-aripiprazole in pediatric patients, 10 to 17 years of age, were similar to those in adults after correcting for the differences in body weight [see Clinical Pharmacology (12.3)].

Schizophrenia

Safety and effectiveness in pediatric patients with schizophrenia were established in a 6-week, placebo-controlled clinical trial in 202 pediatric patients aged 13 to 17 years [see Dosage and Administration (2.1), Adverse Reactions (6.1), and Clinical Studies (14.1)]. Although maintenance efficacy in pediatric patients has not been systematically evaluated, maintenance efficacy can be extrapolated from adult data along with comparisons of aripiprazole pharmacokinetic parameters in adult and pediatric patients.

Bipolar I Disorder

Safety and effectiveness in pediatric patients with bipolar mania were established in a 4-week, placebo-controlled clinical trial in 197 pediatric patients aged 10 to 17 years [see Dosage and Administration (2.2), Adverse Reactions (6.1), and Clinical Studies (14.2)]. Although maintenance efficacy in pediatric patients has not been systematically evaluated, maintenance efficacy can be extrapolated from adult data along with comparisons of aripiprazole pharmacokinetic parameters in adult and pediatric patients.

The efficacy of adjunctive ABILIFY with concomitant lithium or valproate in the treatment of manic or mixed episodes in pediatric patients has not been systematically evaluated. However, such efficacy and lack of pharmacokinetic interaction between aripiprazole and lithium or valproate can be extrapolated from adult data, along with comparisons of aripiprazole pharmacokinetic parameters in adult and pediatric patients.

Irritability Associated with Autistic Disorder

Safety and effectiveness in pediatric patients demonstrating irritability associated with autistic disorder were established in two 8-week, placebo-controlled clinical trials in 212 pediatric patients aged 6 to 17 years [see Indications and Usage (1), Dosage and Administration (2.4), Adverse Reactions (6.1), and Clinical Studies (14.4)]. A maintenance trial was conducted in pediatric patients (6 to 17 years of age) with irritability associated with autistic disorder. The first phase of this trial was an open-label, flexibly dosed (aripiprazole 2 to 15 mg/day) phase in which patients were stabilized (defined as >25% improvement on the ABC-I subscale, and a CGI-I rating of "much improved" or "very much improved") on ABILIFY for 12 consecutive weeks. Overall, 85 patients were stabilized and entered the second, 16-week, double-blind phase where they were randomized to either continue ABILIFY treatment or switch to placebo. In this trial, the efficacy of ABILIFY for the maintenance treatment of irritability associated with autistic disorder was not established.

Tourette's Disorder

Safety and effectiveness of aripiprazole in pediatric patients with Tourette's Disorder were established in one 8-week (aged 7 to 17 years) and one 10-week trial (aged 6 to 18 years) in 194 pediatric patients [see Dosage and Administration (2.5), Adverse Reactions (6.1), and Clinical Studies (14.5)]. Maintenance efficacy in pediatric patients has not been systematically evaluated.

Juvenile Animal Studies

Aripiprazole in juvenile rats caused mortality, CNS clinical signs, impaired memory and learning, and delayed sexual maturation when administered at oral doses of 10, 20, 40 mg/kg/day from weaning (21 days old) through maturity (80 days old). At 40 mg/kg/day, mortality, decreased activity, splayed hind limbs, hunched posture, ataxia, tremors and other CNS signs were observed in both genders. In addition, delayed sexual maturation was observed in males. At all doses and in a dose-dependent manner, impaired memory and learning, increased motor activity, and histopathology changes in the pituitary (atrophy), adrenals (adrenocortical hypertrophy), mammary glands (hyperplasia and increased secretion), and female reproductive organs (vaginal mucification, endometrial atrophy, decrease in ovarian corpora lutea) were observed. The changes in female reproductive organs were considered secondary to the increase in prolactin serum levels. A No Observed Adverse Effect Level (NOAEL) could not be determined and, at the lowest tested dose of 10 mg/kg/day, there is no safety margin relative to the systemic exposures (AUC0-24) for aripiprazole or its major active metabolite in adolescents at the maximum recommended pediatric dose of 15 mg/day. All drug-related effects were reversible after a 2-month recovery period, and most of the drug effects in juvenile rats were also observed in adult rats from previously conducted studies.

Aripiprazole in juvenile dogs (2 months old) caused CNS clinical signs of tremors, hypoactivity, ataxia, recumbency and limited use of hind limbs when administered orally for 6 months at 3, 10, 30 mg/kg/day. Mean body weight and weight gain were decreased up to 18% in females in all drug groups relative to control values. A NOAEL could not be determined and, at the lowest tested dose of 3 mg/kg/day, there is no safety margin relative to the systemic exposures (AUC0-24) for aripiprazole or its major active metabolite in adolescents at the maximum recommended pediatric dose of 15 mg/day. All drug-related effects were reversible after a 2-month recovery period.

8.5 Geriatric Use

No dosage adjustment is recommended for elderly patients [see Boxed Warning, Warnings and Precautions (5.1), and Clinical Pharmacology (12.3)].

Of the 13,543 patients treated with oral ABILIFY in clinical trials, 1,073 (8%) were ≥65 years old and 799 (6%) were ≥75 years old. Placebo-controlled studies of ABILIFY in schizophrenia, bipolar mania, or major depressive disorder did not include sufficient numbers of patients aged 65 and over to determine whether they respond differently from younger patients.

ABILIFY is not approved for the treatment of patients with psychosis associated with Alzheimer's disease [see Boxed Warning and Warnings and Precautions (5.1)].

8.6 CYP2D6 Poor Metabolizers

Dosage adjustment is recommended in known CYP2D6 poor metabolizers due to high aripiprazole concentrations. Approximately 8% of Caucasians and 3 to 8% of Black/African Americans cannot metabolize CYP2D6 substrates and are classified as poor metabolizers (PM) [see Dosage and Administration (2.6) and Clinical Pharmacology (12.3)].

8.7 Hepatic and Renal Impairment

No dosage adjustment for ABILIFY is required on the basis of a patient's hepatic function (mild to severe hepatic impairment, Child-Pugh score between 5 and 15), or renal function (mild to severe renal impairment, glomerular filtration rate between 15 and 90 mL/minute) [see Clinical Pharmacology (12.3)].

8.8 Other Specific Populations

No dosage adjustment for ABILIFY is required on the basis of a patient's sex, race, or smoking status [see Clinical Pharmacology (12.3)].

9 DRUG ABUSE AND DEPENDENCE

9.1 Controlled Substance

ABILIFY is not a controlled substance.

9.2 Abuse

ABILIFY has not been systematically studied in humans for its potential for abuse, tolerance, or physical dependence. Consequently, patients should be evaluated carefully for a history of drug abuse, and such patients should be observed closely for signs of ABILIFY misuse or abuse (e.g., development of tolerance, increases in dose, drug-seeking behavior).

9.3 Dependence

In physical dependence studies in monkeys, withdrawal symptoms were observed upon abrupt cessation of dosing. While the clinical trials did not reveal any tendency for any drug-seeking behavior, these observations were not systematic and it is not possible to predict on the basis of this limited experience the extent to which a CNS-active drug will be misused, diverted, and/or abused once marketed.

10 OVERDOSAGE

MedDRA terminology has been used to classify the adverse reactions.

Human Experience

In clinical trials and in postmarketing experience, adverse reactions of deliberate or accidental overdosage with oral ABILIFY have been reported worldwide. These include overdoses with ABILIFY alone and in combination with other substances. No fatality was reported with ABILIFY alone. The largest known dose with a known outcome involved acute ingestion of 1,260 mg of ABILIFY (42 times the maximum recommended daily dose) by a patient who fully recovered. Deliberate or accidental overdosage was also reported in children (age 12 years and younger) involving ABILIFY ingestions up to 195 mg with no fatalities.

Common adverse reactions (reported in at least 5% of all overdose cases) reported with oral ABILIFY overdosage (alone or in combination with other substances) include vomiting, somnolence, and tremor. Other clinically important signs and symptoms observed in one or more patients with ABILIFY overdoses (alone or with other substances) include acidosis, aggression, aspartate aminotransferase increased, atrial fibrillation, bradycardia, coma, confusional state, convulsion, blood creatine phosphokinase increased, depressed level of consciousness, hypertension, hypokalemia, hypotension, lethargy, loss of consciousness, QRS complex prolonged, QT prolonged, pneumonia aspiration, respiratory arrest, status epilepticus, and tachycardia.

Management of Overdosage

No specific information is available on the treatment of overdose with ABILIFY. An electrocardiogram should be obtained in case of overdosage and if QT interval prolongation is present, cardiac monitoring should be instituted. Otherwise, management of overdose should concentrate on supportive therapy, maintaining an adequate airway, oxygenation and ventilation, and management of symptoms. Close medical supervision and monitoring should continue until the patient recovers.

Charcoal: In the event of an overdose of ABILIFY, an early charcoal administration may be useful in partially preventing the absorption of aripiprazole. Administration of 50 g of activated charcoal, one hour after a single 15 mg dose of ABILIFY, decreased the mean AUC and Cmax of aripiprazole by 50%.

Hemodialysis: Although there is no information on the effect of hemodialysis in treating an overdose with ABILIFY, hemodialysis is unlikely to be useful in overdose management since aripiprazole is highly bound to plasma proteins.

11 DESCRIPTION

Aripiprazole is an atypical antipsychotic drug that is available as ABILIFY® (aripiprazole) Tablets. Aripiprazole is 7-[4-[4-(2,3-dichlorophenyl)-1-piperazinyl]butoxy]-3,4-dihydrocarbostyril. The empirical formula is C23H27Cl2N3O2 and its molecular weight is 448.38. The chemical structure is:

ABILIFY Tablets are available in 2 mg, 5 mg, 10 mg, 15 mg, 20 mg, and 30 mg strengths. Inactive ingredients include cornstarch, hydroxypropyl cellulose, lactose monohydrate, magnesium stearate, and microcrystalline cellulose. Colorants include ferric oxide (yellow or red) and FD&C Blue No. 2 Aluminum Lake.

12 CLINICAL PHARMACOLOGY

12.1 Mechanism of Action

The mechanism of action of aripiprazole in schizophrenia or bipolar mania, is unclear. However, the efficacy of aripiprazole in the listed indications could be mediated through a combination of partial agonist activity at D2 and 5-HT1A receptors and antagonist activity at 5-HT2A receptors.

12.2 Pharmacodynamics

Aripiprazole exhibits high affinity for dopamine D2 and D3, serotonin 5-HT1A and 5-HT2A receptors (Ki values of 0.34 nM, 0.8 nM, 1.7 nM, and 3.4 nM, respectively), moderate affinity for dopamine D4, serotonin 5-HT2C and 5-HT7, alpha1-adrenergic and histamine H1 receptors (Ki values of 44 nM, 15 nM, 39 nM, 57 nM, and 61 nM, respectively), and moderate affinity for the serotonin reuptake site (Ki=98 nM). Aripiprazole has no appreciable affinity for cholinergic muscarinic receptors (IC50>1000 nM).

12.3 Pharmacokinetics

ABILIFY activity is presumably primarily due to the parent drug, aripiprazole, and to a lesser extent, to its major metabolite, dehydro-aripiprazole, which has been shown to have affinities for D2 receptors similar to the parent drug and represents 40% of the parent drug exposure in plasma. The mean elimination half-lives are about 75 hours and 94 hours for aripiprazole and dehydro-aripiprazole, respectively. Steady-state concentrations are attained within 14 days of dosing for both active moieties. Aripiprazole accumulation is predictable from single-dose pharmacokinetics. At steady-state, the pharmacokinetics of aripiprazole is dose-proportional. Elimination of aripiprazole is mainly through hepatic metabolism involving two P450 isozymes, CYP2D6 and CYP3A4. For CYP2D6 poor metabolizers, the mean elimination half-life for aripiprazole is about 146 hours.

Absorption

Aripiprazole is well absorbed after administration of the tablet, with peak plasma concentrations occurring within 3 hours to 5 hours; the absolute oral bioavailability of the tablet formulation is 87%. ABILIFY can be administered with or without food. Administration of a 15 mg ABILIFY tablet with a standard high-fat meal did not significantly affect the Cmax or AUC of aripiprazole or its active metabolite, dehydro-aripiprazole, but delayed Tmax by 3 hours for aripiprazole and 12 hours for dehydro-aripiprazole.

Distribution

The steady-state volume of distribution of aripiprazole following intravenous administration is high (404 L or 4.9 L/kg), indicating extensive extravascular distribution. At therapeutic concentrations, aripiprazole and its major metabolite are greater than 99% bound to serum proteins, primarily to albumin. In healthy human volunteers administered 0.5 to 30 mg/day aripiprazole for 14 days, there was dose-dependent D2 receptor occupancy indicating brain penetration of aripiprazole in humans.

Metabolism and Elimination

Metabolism

Aripiprazole is metabolized primarily by three biotransformation pathways: dehydrogenation, hydroxylation, and N-dealkylation. Based on in vitro studies, CYP3A4 and CYP2D6 enzymes are responsible for dehydrogenation and hydroxylation of aripiprazole, and N-dealkylation is catalyzed by CYP3A4. Aripiprazole is the predominant drug moiety in the systemic circulation. At steady-state, dehydro-aripiprazole, the active metabolite, represents about 40% of aripiprazole AUC in plasma.

Excretion

Following a single oral dose of [^14C]-labeled aripiprazole, approximately 25% and 55% of the administered radioactivity was recovered in the urine and feces, respectively. Less than 1% of unchanged aripiprazole was excreted in the urine and approximately 18% of the dose was recovered unchanged in the feces.

Drug Interaction Studies

Effect of other drugs on the exposures of aripiprazole and dehydro-aripiprazole are summarized in Figure 1 and Figure 2, respectively. Based on simulation, a 4.5-fold increase in mean Cmax and AUC values at steady-state is expected when extensive metabolizers of CYP2D6 are administered with both strong CYP2D6 and CYP3A4 inhibitors. A 3-fold increase in mean Cmax and AUC values at steady-state is expected in poor metabolizers of CYP2D6 administered with strong CYP3A4 inhibitors.

Figure 1: The Effect of Other Drugs on Aripiprazole Pharmacokinetics

Figure 2: The Effect of Other Drugs on Dehydro-Aripiprazole Pharmacokinetics

The effect of ABILIFY on the exposures of other drugs are summarized in Figure 3. A population PK analysis in patients with major depressive disorder showed no substantial change in plasma concentrations of fluoxetine (20 or 40 mg/day), paroxetine CR (37.5 or 50 mg/day), or sertraline (100 or 150 mg/day) dosed to steady-state. The steady-state plasma concentrations of fluoxetine and norfluoxetine increased by about 18% and 36%, respectively, and concentrations of paroxetine decreased by about 27%. The steady-state plasma concentrations of sertraline and desmethylsertraline were not substantially changed when these antidepressant therapies were coadministered with aripiprazole.

Figure 3: The Effect of ABILIFY on Pharmacokinetics of Other Drugs

Specific Populations

Exposure of aripiprazole and dehydro-aripiprazole in specific populations are summarized in Figure 4 and Figure 5, respectively. In addition, in pediatric patients (10 to 17 years of age) administered with ABILIFY (20 mg to 30 mg), the body weight corrected aripiprazole clearance was similar to the adults.

Figure 4: Effect of Intrinsic Factors on Aripiprazole Pharmacokinetics

Figure 5: Effect of Intrinsic Factors on Dehydro-aripiprazole Pharmacokinetics

13 NONCLINICAL TOXICOLOGY

13.1 Carcinogenesis, Mutagenesis, Impairment of Fertility

Carcinogenesis

Lifetime carcinogenicity studies were conducted in ICR mice, F344 rats, and Sprague-Dawley (SD) rats. Aripiprazole was administered for 2 years in the diet at doses of 1, 3, 10, and 30 mg/kg/day to ICR mice and 1, 3, and 10 mg/kg/day to F344 rats (0.2, 0.5, 2 and 5 times and 0.3, 1 and 3 times the MRHD of 30 mg/day based on mg/m^2 body surface area, respectively). In addition, SD rats were dosed orally for 2 years at 10, 20, 40, and 60 mg/kg/day, which are 3, 6, 13 and 19 times the MRHD based on mg/m^2 body surface area. Aripiprazole did not induce tumors in male mice or male rats. In female mice, the incidences of pituitary gland adenomas and mammary gland adenocarcinomas and adenoacanthomas were increased at dietary doses of 3 to 30 mg/kg/day (0.5 to 5 times the MRHD). In female rats, the incidence of mammary gland fibroadenomas was increased at a dietary dose of 10 mg/kg/day (3 times the MRHD); and the incidences of adrenocortical carcinomas and combined adrenocortical adenomas/carcinomas were increased at an oral dose of 60 mg/kg/day (19 times the MRHD).

An increase in mammary, pituitary, and endocrine pancreas neoplasms has been found in rodents after chronic administration of other antipsychotic drugs and is considered to be mediated by prolonged dopamine D2-receptor antagonism and hyperprolactinemia. Serum prolactin was not measured in the aripiprazole carcinogenicity studies. However, increases in serum prolactin levels were observed in female mice in a 13-week dietary study at the doses associated with mammary gland and pituitary tumors. Serum prolactin was not increased in female rats in 4 week and 13-week dietary studies at the dose associated with mammary gland tumors. The relevance for human risk of the findings of prolactin-mediated endocrine tumors in rodents is unclear.

Mutagenesis

The mutagenic potential of aripiprazole was tested in the in vitro bacterial reverse-mutation assay, the in vitro bacterial DNA repair assay, the in vitro forward gene mutation assay in mouse lymphoma cells, the in vitro chromosomal aberration assay in Chinese hamster lung (CHL) cells, the in vivo micronucleus assay in mice, and the unscheduled DNA synthesis assay in rats. Aripiprazole and a metabolite (2,3-DCPP) were clastogenic in the in vitro chromosomal aberration assay in CHL cells with and without metabolic activation. The metabolite, 2,3-DCPP, increased numerical aberrations in the in vitro assay in CHL cells in the absence of metabolic activation. A positive response was obtained in the in vivo micronucleus assay in mice; however, the response was due to a mechanism not considered relevant to humans.

Impairment of Fertility

Female rats were treated orally with aripiprazole from 2 weeks prior to mating through gestation Day 7 at doses of 2, 6, and 20 mg/kg/day, which are 0.6, 2, and 6 times the MRHD of 30 mg/day based on mg/m^2 body surface area. Estrus cycle irregularities and increased corpora lutea were seen at all doses, but no impairment of fertility was seen. Increased pre-implantation loss was seen at 2 and 6 times the MRHD, and decreased fetal weight was seen at 6 times the MRHD.

Male rats were treated orally with aripiprazole from 9 weeks prior to mating through mating at doses of 20, 40, and 60 mg/kg/day, which are 6, 13, and 19 times the MRHD of 30 mg/day based on mg/m^2 body surface area. Disturbances in spermatogenesis were seen at 19 times the MRHD and prostate atrophy was seen at 13 and 19 times the MRHD without impairment of fertility.

13.2 Animal Toxicology and/or Pharmacology

Aripiprazole produced retinal degeneration in albino rats in a 26-week chronic toxicity study at a dose of 60 mg/kg/day and in a 2-year carcinogenicity study at doses of 40 and 60 mg/kg/day which are 13 and 19 times the MRHD of 30 mg/day based on mg/m^2 body surface area. Evaluation of the retinas of albino mice and of monkeys did not reveal evidence of retinal degeneration. Additional studies to further evaluate the mechanism have not been performed. The relevance of this finding to human risk is unknown.

14 CLINICAL STUDIES

Efficacy of ABILIFY was established in the following adequate and well-controlled trials:

- Four short-term trials and one maintenance trial in adult patients and one short-term trial in adolescents (ages 13 to 17 years) with schizophrenia [see Clinical Studies (14.1)]
- Four short-term monotherapy trials and one 6-week adjunctive trial in adult patients and one short-term monotherapy trial in pediatric patients (ages 10 to 17 years) with manic or mixed episodes [see Clinical Studies (14.2)]
- One maintenance monotherapy trial and one maintenance adjunctive trial in adult patients with bipolar I disorder [see Clinical Studies (14.2)]
- Two short-term trials in adult patients with MDD who had an inadequate response to antidepressant therapy during the current episode [see Clinical Studies (14.3)]
- Two short-term trials in pediatric patients (ages 6 to 17 years) for the treatment of irritability associated with autistic disorder [see Clinical Studies (14.4)]
- Two short-term trials in pediatric patients (ages 6 to 18 years) with Tourette's Disorder [see Clinical Studies (14.5)]

14.1 Schizophrenia

Adults

The efficacy of ABILIFY in the treatment of schizophrenia was evaluated in five short-term (4-week and 6-week), placebo-controlled trials of acutely relapsed inpatients who predominantly met DSM-III/IV criteria for schizophrenia. Four of the five trials were able to distinguish ABILIFY from placebo, but one study, the smallest, did not. Three of these studies also included an active control group consisting of either risperidone (one trial) or haloperidol (two trials), but they were not designed to allow for a comparison of ABILIFY and the active comparators.

In the four positive trials for ABILIFY, four primary measures were used for assessing psychiatric signs and symptoms. Efficacy was evaluated using the total score on the Positive and Negative Syndrome Scale (PANSS). The PANSS is a 30-item scale that measures positive symptoms of schizophrenia (7 items), negative symptoms of schizophrenia (7 items), and general psychopathology (16 items), each rated on a scale of 1 (absent) to 7 (extreme); total PANSS scores range from 30 to 210. The Clinical Global Impression (CGI) assessment reflects the impression of a skilled observer, fully familiar with the manifestations of schizophrenia, about the overall clinical state of the patient.

In a 4-week trial (n=414) comparing two fixed doses of ABILIFY (15 or 30 mg/day) to placebo, both doses of ABILIFY were superior to placebo in the PANSS total score (Study 1 in Table 23), PANSS positive subscale, and CGI-severity score. In addition, the 15 mg dose was superior to placebo in the PANSS negative subscale.

In a 4-week trial (n=404) comparing two fixed doses of ABILIFY (20 or 30 mg/day) to placebo, both doses of ABILIFY were superior to placebo in the PANSS total score (Study 2 in Table 23), PANSS positive subscale, PANSS negative subscale, and CGI-severity score.

In a 6-week trial (n=420) comparing three fixed doses of ABILIFY (10, 15, or 20 mg/day) to placebo, all three doses of ABILIFY were superior to placebo in the PANSS total score (Study 3 in Table 23), PANSS positive subscale, and the PANSS negative subscale.

In a 6-week trial (n=367) comparing three fixed doses of ABILIFY (2, 5, or 10 mg/day) to placebo, the 10 mg dose of ABILIFY was superior to placebo in the PANSS total score (Study 4 in Table 23), the primary outcome measure of the study. The 2 mg and 5 mg doses did not demonstrate superiority to placebo on the primary outcome measure.

Thus, the efficacy of 10 mg, 15 mg, 20 mg, and 30 mg daily doses was established in two studies for each dose. Among these doses, there was no evidence that the higher dose groups offered any advantage over the lowest dose group of these studies.

An examination of population subgroups did not reveal any clear evidence of differential responsiveness on the basis of age, gender, or race.

A longer-term trial enrolled 310 inpatients or outpatients meeting DSM-IV criteria for schizophrenia who were, by history, symptomatically stable on other antipsychotic medications for periods of 3 months or longer. These patients were discontinued from their antipsychotic medications and randomized to ABILIFY 15 mg/day or placebo for up to 26 weeks of observation for relapse. Relapse during the double-blind phase was defined as CGI-Improvement score of ≥5 (minimally worse), scores ≥5 (moderately severe) on the hostility or uncooperativeness items of the PANSS, or ≥20% increase in the PANSS total score. Patients receiving ABILIFY 15 mg/day experienced a significantly longer time to relapse over the subsequent 26 weeks compared to those receiving placebo (Study 5 in Figure 6).

Pediatric Patients

The efficacy of ABILIFY in the treatment of schizophrenia in pediatric patients (13 to 17 years of age) was evaluated in one 6-week, placebo-controlled trial of outpatients who met DSM-IV criteria for schizophrenia and had a PANSS score ≥70 at baseline. In this trial (n=302) comparing two fixed doses of ABILIFY (10 or 30 mg/day) to placebo, ABILIFY was titrated starting from 2 mg/day to the target dose in 5 days in the 10 mg/day treatment arm and in 11 days in the 30 mg/day treatment arm. Both doses of ABILIFY were superior to placebo in the PANSS total score (Study 6 in Table 23 the primary outcome measure of the study. The 30 mg/day dosage was not shown to be more efficacious than the 10 mg/day dose. Although maintenance efficacy in pediatric patients has not been systematically evaluated, maintenance efficacy can be extrapolated from adult data along with comparisons of aripiprazole pharmacokinetic parameters in adult and pediatric patients.

Table 23: Schizophrenia Studies
Study Number | Treatment Group | Primary Efficacy Measure: PANSS
Study Number | Treatment Group | Mean Baseline Score (SD) | LS Mean Change from Baseline (SE) | Placebo-subtracted Difference [Difference (drug minus placebo) in least-squares mean change from baseline.] (95% CI)
Study 1 | Treatment Group | ABILIFY (15 mg/day) [Doses statistically significantly superior to placebo.] | 98.5 (17.2) | -15.5 (2.40) | -12.6 (-18.9, -6.2)
Study 1 | ABILIFY (30 mg/day) | 99.0 (19.2) | -11.4 (2.39) | -8.5 (-14.8, -2.1)
Study 1 | Placebo | 100.2 (16.5) | -2.9 (2.36) | --
Study 2 | ABILIFY (20 mg/day) | 92.6 (19.5) | -14.5 (2.23) | -9.6 (-15.4, -3.8)
Study 2 | ABILIFY (30 mg/day) | 94.2 (18.5) | -13.9 (2.24) | -9.0 (-14.8, -3.1)
Study 2 | Placebo | 94.3 (18.5) | -5.0 (2.17) | --
Study 3 | ABILIFY (10 mg/day) | 92.7 (19.5) | -15.0 (2.38) | -12.7 (-19.00, -6.41)
Study 3 | ABILIFY (15 mg/day) | 93.2 (21.6) | -11.7 (2.38) | -9.4 (-15.71, -3.08)
Study 3 | ABILIFY (20 mg/day) | 92.5 (20.9) | -14.4 (2.45) | -12.1 (-18.53, -5.68)
Study 3 | Placebo | 92.3 (21.8) | -2.3 (2.35) | --
Study 4 | ABILIFY (2 mg/day) | 90.7 (14.5) | -8.2 (1.90) | -2.9 (-8.29, 2.47)
Study 4 | ABILIFY (5 mg/day) | 92.0 (12.6) | -10.6 (1.93) | -5.2 (-10.7, 0.19)
Study 4 | ABILIFY (10 mg/day) | 90.0 (11.9) | -11.3 (1.88) | -5.9 (-11.3, -0.58)
Study 4 | Placebo | 90.8 (13.3) | -5.3 (1.97) | --
Study 6 (Pediatric, 13 to 17 years) | ABILIFY (10 mg/day) | 93.6 (15.7) | -26.7 (1.91) | -5.5 (-10.7, -0.21)
Study 6 (Pediatric, 13 to 17 years) | ABILIFY (30 mg/day) | 94.0 (16.1) | -28.6 (1.92) | -7.4 (-12.7, -2.13)
Study 6 (Pediatric, 13 to 17 years) | Placebo | 94.6 (15.6) | -21.2 (1.93) | --
SD: standard deviation; SE: standard error; LS Mean: least-squares mean; CI: unadjusted confidence interval.

Figure 6: Kaplan-Meier Estimation of Cumulative Proportion of Patients with Relapse (Schizophrenia Study 5)

14.2 Bipolar Disorder

Acute Treatment of Manic and Mixed Episodes

Adults

Monotherapy

The efficacy of ABILIFY as monotherapy in the acute treatment of manic episodes was established in four 3-week, placebo-controlled trials in hospitalized patients who met the DSM-IV criteria for bipolar I disorder with manic or mixed episodes. These studies included patients with or without psychotic features and two of the studies also included patients with or without a rapid-cycling course.

The primary instrument used for assessing manic symptoms was the Young Mania Rating Scale (Y-MRS), an 11 item clinician-rated scale traditionally used to assess the degree of manic symptomatology in a range from 0 (no manic features) to 60 (maximum score). A key secondary instrument included the Clinical Global Impression-Bipolar (CGI-BP) Scale.

In the four positive, 3-week, placebo-controlled trials (n=268; n=248; n=480; n=485) which evaluated ABILIFY in a range of 15 mg to 30 mg, once daily (with a starting dose of 30 mg/day in two studies and 15 mg/day in two studies), ABILIFY was superior to placebo in the reduction of Y-MRS total score (Studies 1 to 4 in Table 24) and CGI-BP Severity of Illness score (mania). In the two studies with a starting dose of 15 mg/day, 48% and 44% of patients were on 15 mg/day at endpoint. In the two studies with a starting dose of 30 mg/day, 86% and 85% of patients were on 30 mg/day at endpoint.

Adjunctive Therapy

The efficacy of adjunctive ABILIFY with concomitant lithium or valproate in the treatment of manic or mixed episodes was established in a 6-week, placebo-controlled study (n=384) with a 2-week lead-in mood stabilizer monotherapy phase in adult patients who met DSM-IV criteria for bipolar I disorder. This study included patients with manic or mixed episodes and with or without psychotic features.

Patients were initiated on open-label lithium (0.6 to 1.0 mEq/L) or valproate (50 to 125 mcg/mL) at therapeutic serum levels and remained on stable doses for 2 weeks. At the end of 2 weeks, patients demonstrating inadequate response (Y-MRS total score ≥16 and ≤25% improvement on the Y-MRS total score) to lithium or valproate were randomized to receive either ABILIFY (15 mg/day or an increase to 30 mg/day as early as Day 7) or placebo as adjunctive therapy with open-label lithium or valproate. In the 6-week, placebo-controlled phase, adjunctive ABILIFY starting at 15 mg/day with concomitant lithium or valproate (in a therapeutic range of 0.6 to 1.0 mEq/L or 50 to 125 mcg/mL, respectively) was superior to lithium or valproate with adjunctive placebo in the reduction of the Y-MRS total score (Study 5 in Table 24) and CGI-BP Severity of Illness score (mania). Seventy-one percent of the patients coadministered valproate and 62% of the patients coadministered lithium were on 15 mg/day at 6-week endpoint.

Pediatric Patients

The efficacy of ABILIFY in the treatment of bipolar I disorder in pediatric patients (10 to 17 years of age) was evaluated in one 4-week, placebo-controlled trial (n=296) of outpatients who met DSM-IV criteria for bipolar I disorder manic or mixed episodes with or without psychotic features and had a Y-MRS score ≥20 at baseline. This double-blind, placebo-controlled trial compared two fixed doses of ABILIFY (10 or 30 mg/day) to placebo. The ABILIFY dose was started at 2 mg/day, which was titrated to 5 mg/day after 2 days, and to the target dose in 5 days in the 10 mg/day treatment arm, and in 13 days in the 30 mg/day treatment arm. Both doses of ABILIFY were superior to placebo in change from baseline to Week 4 on the Y-MRS total score (Study 6 in Table 24).

Table 24: Bipolar Studies
Study Number | Treatment Group | Primary Efficacy Measure: Y-MRS
Study Number | Treatment Group | Mean Baseline Score (SD) | LS Mean Change from Baseline (SE) | Placebo-subtracted Difference [Difference (drug minus placebo) in least-squares mean change from baseline.] (95% CI)
Study 1 | ABILIFY (30/15 mg/day) [Doses statistically significantly superior to placebo.] | 29.0 (5.9) | -12.52 (1.05) | -5.33 (-7.90, -2.76)
Study 1 | Placebo | 28.5 (4.6) | -7.19 (1.07) | --
Study 2 | ABILIFY (30/15 mg/day) | 27.8 (5.7) | -8.15 (1.23) | -4.80 (-7.80, -1.80)
Study 2 | Placebo | 29.1 (6.9) | -3.35 (1.22) | --
Study 3 | ABILIFY (15 to 30 mg/day) | 28.5 (5.6) | -12.64 (0.84) | -3.63 (-5.75, -1.51)
Study 3 | Placebo | 28.9 (5.9) | 9.01 (0.81) | --
Study 4 | ABILIFY (15 to 30 mg/day) | 28.0 (5.8) | -11.98 (0.80) | -2.28 (-4.44, -0.11)
Study 4 | Placebo | 28.3 (5.8) | -9.70 (0.83) | --
Study 5 | ABILIFY (15 or 30 mg/day) + Lithium/Valproate | 23.2 (5.7) | -13.31 (0.50) | -2.62 (-4.29, -0.95)
Study 5 | Placebo + Lithium/Valproate | 23.0 (4.9) | -10.70 (0.69) | --
Study 6 (Pediatric, 10 to 17 years) | ABILIFY (10 mg/day) | 29.8 (6.5) | -14.2 (0.89) | -5.99 (-8.49, -3.50)
Study 6 (Pediatric, 10 to 17 years) | ABILIFY (30 mg/day) | 29.5 (6.3) | -16.5 (0.87) | -8.26 (-10.7, -5.77)
Study 6 (Pediatric, 10 to 17 years) | Placebo | 30.7 (6.8) | -8.2 (0.91) | --
SD: standard deviation; SE: standard error; LS Mean: least-squares mean; CI: unadjusted confidence interval.

Maintenance Treatment of Bipolar I Disorder

Monotherapy Maintenance Therapy

A maintenance trial was conducted in adult patients meeting DSM-IV criteria for bipolar I disorder with a recent manic or mixed episode who had been stabilized on open-label ABILIFY and who had maintained a clinical response for at least 6 weeks. The first phase of this trial was an open-label stabilization period in which inpatients and outpatients were clinically stabilized and then maintained on open-label ABILIFY (15 or 30 mg/day, with a starting dose of 30 mg/day) for at least 6 consecutive weeks. One hundred sixty-one outpatients were then randomized in a double-blind fashion, to either the same dose of ABILIFY they were on at the end of the stabilization and maintenance period or placebo and were then monitored for manic or depressive relapse. During the randomization phase, ABILIFY was superior to placebo on time to the number of combined affective relapses (manic plus depressive), the primary outcome measure for this study (Study 7 in Figure 7). A total of 55 mood events were observed during the double-blind treatment phase. Nineteen were from the ABILIFY group and 36 were from the placebo group. The number of observed manic episodes in the ABILIFY group (6) were fewer than that in the placebo group (19), while the number of depressive episodes in the ABILIFY group (9) was similar to that in the placebo group (11).

An examination of population subgroups did not reveal any clear evidence of differential responsiveness on the basis of age and gender; however, there were insufficient numbers of patients in each of the ethnic groups to adequately assess inter-group differences.

Figure 7: Kaplan-Meier Estimation of Cumulative Proportion of Patients with Relapse (Bipolar Study 7)

Adjunctive Maintenance Therapy

An adjunctive maintenance trial was conducted in adult patients meeting DSM-IV criteria for bipolar I disorder with a recent manic or mixed episode. Patients were initiated on open-label lithium (0.6 to 1.0 mEq/L) or valproate (50 to 125 mcg/mL) at therapeutic serum levels and remained on stable doses for 2 weeks. At the end of 2 weeks, patients demonstrating inadequate response (Y-MRS total score ≥16 and ≤35% improvement on the Y-MRS total score) to lithium or valproate received ABILIFY with a starting dose of 15 mg/day with the option to increase to 30 mg or reduce to 10 mg as early as Day 4, as adjunctive therapy with open-label lithium or valproate. Prior to randomization, patients on the combination of single-blind ABILIFY and lithium or valproate were required to maintain stability (Y-MRS and MADRS total scores ≤12) for 12 consecutive weeks. Three hundred thirty-seven patients were then randomized in a double-blind fashion, to either the same dose of ABILIFY they were on at the end of the stabilization period or placebo plus lithium or valproate and were then monitored for manic, mixed, or depressive relapse for a maximum of 52 weeks. ABILIFY was superior to placebo on the primary endpoint, time from randomization to relapse to any mood event (Study 8 in Figure 8). A mood event was defined as hospitalization for a manic, mixed, or depressive episode, study discontinuation due to lack of efficacy accompanied by Y-MRS score >16 and/or a MADRS >16, or an SAE of worsening disease accompanied by Y-MRS score >16 and/or a MADRS >16. A total of 68 mood events were observed during the double-blind treatment phase. Twenty-five were from the ABILIFY group and 43 were from the placebo group. The number of observed manic episodes in the ABILIFY group (7) were fewer than that in the placebo group (19), while the number of depressive episodes in the ABILIFY group (14) was similar to that in the placebo group (18). The Kaplan-Meier curves of the time from randomization to relapse to any mood event during the 52-week, double-blind treatment phase for ABILIFY and placebo groups are shown in Figure 8.

An examination of population subgroups did not reveal any clear evidence of differential responsiveness on the basis of age and gender; however, there were insufficient numbers of patients in each of the ethnic groups to adequately assess inter-group differences.

Figure 8: Kaplan-Meier Estimation of Cumulative Proportion of Patients with Relapse to Any Mood Event (Bipolar Study 8)

14.3 Adjunctive Treatment of Major Depressive Disorder

Adults

The efficacy of ABILIFY in the adjunctive treatment of major depressive disorder (MDD) was demonstrated in two short-term (6-week), placebo-controlled trials of adult patients meeting DSM-IV criteria for MDD who had had an inadequate response to prior antidepressant therapy (1 to 3 courses) in the current episode and who had also demonstrated an inadequate response to 8 weeks of prospective antidepressant therapy (paroxetine controlled-release, venlafaxine extended-release, fluoxetine, escitalopram, or sertraline). Inadequate response for prospective treatment was defined as less than 50% improvement on the 17-item version of the Hamilton Depression Rating Scale (HAMD17), minimal HAMD17 score of 14, and a Clinical Global Impressions Improvement rating of no better than minimal improvement. Inadequate response to prior treatment was defined as less than 50% improvement as perceived by the patient after a minimum of 6 weeks of antidepressant therapy at or above the minimal effective dose.

The primary instrument used for assessing depressive symptoms was the Montgomery-Asberg Depression Rating Scale (MADRS), a 10-item clinician-rated scale used to assess the degree of depressive symptomatology. The key secondary instrument was the Sheehan Disability Scale (SDS), a 3-item self-rated instrument used to assess the impact of depression on three domains of functioning with each item scored from 0 (not at all) to 10 (extreme).

In the two trials (n=381, n=362), ABILIFY was superior to placebo in reducing mean MADRS total scores (Studies 1, 2 in Table 25). In one study, ABILIFY was also superior to placebo in reducing the mean SDS score.

In both trials, patients received ABILIFY adjunctive to antidepressants at a dose of 5 mg/day. Based on tolerability and efficacy, doses could be adjusted by 5 mg increments, one week apart. Allowable doses were: 2, 5, 10, 15 mg/day, and for patients who were not on potent CYP2D6 inhibitors fluoxetine and paroxetine, 20 mg/day. The mean final dose at the end point for the two trials was 10.7 and 11.4 mg/day.

An examination of population subgroups did not reveal evidence of differential response based on age, choice of prospective antidepressant, or race. With regard to gender, a smaller mean reduction on the MADRS total score was seen in males than in females.

Table 25: Adjunctive Treatment of Major Depressive Disorder Studies
Study Number | Treatment Group | Primary Efficacy Measure: MADRS
Study Number | Treatment Group | Mean Baseline Score (SD) | LS Mean Change from Baseline (SE) | Placebo-subtracted Difference [Difference (drug minus placebo) in least-squares mean change from baseline.] (95% CI)
Study 1 | ABILIFY (5 to 20 mg/day) [Doses statistically significantly superior to placebo.] + Antidepressant | 25.2 (6.2) | -8.49 (0.66) | -2.84 (-4.53, -1.15)
Study 1 | Placebo + Antidepressant | 27.0 (5.5) | -5.65 (0.64) | --
Study 2 | ABILIFY (5 to 20 mg/day) + Antidepressant | 26.0 (6.0) | -8.78 (0.63) | -3.01 (-4.66, -1.37)
Study 2 | Placebo + Antidepressant | 26.0 (6.5) | -5.77 (0.67) | --
SD: standard deviation; SE: standard error; LS Mean: least-squares mean; CI: unadjusted confidence interval.

14.4 Irritability Associated with Autistic Disorder

Pediatric Patients

The efficacy of ABILIFY in the treatment of irritability associated with autistic disorder was established in two 8-week, placebo-controlled trials in pediatric patients (6 to 17 years of age) who met the DSM-IV criteria for autistic disorder and demonstrated behaviors such as tantrums, aggression, self-injurious behavior, or a combination of these problems. Over 75% of these patients were under 13 years of age.

Efficacy was evaluated using two assessment scales: The Aberrant Behavior Checklist (ABC) and the Clinical Global Impression-Improvement (CGI-I) scale. The primary outcome measure in both trials was the change from baseline to endpoint in the Irritability subscale of the ABC (ABC-I). The ABC-I subscale measured symptoms of irritability in autistic disorder.

The results of these trials are as follows:

In one of the 8-week, placebo-controlled trials, children and adolescents with autistic disorder (n=98), aged 6 to 17 years, received daily doses of placebo or ABILIFY 2 to 15 mg/day. ABILIFY, starting at 2 mg/day with increases allowed up to 15 mg/day based on clinical response, significantly improved scores on the ABC-I subscale and on the CGI-I scale compared with placebo. The mean daily dose of ABILIFY at the end of 8-week treatment was 8.6 mg/day (Study 1 in Table 26).

In the other 8-week, placebo-controlled trial in children and adolescents with autistic disorder (n=218), aged 6 to 17 years, three fixed doses of ABILIFY (5 mg/day, 10 mg/day, or 15 mg/day) were compared to placebo. ABILIFY dosing started at 2 mg/day and was increased to 5 mg/day after one week. After a second week, it was increased to 10 mg/day for patients in the 10 and 15 mg dose arms, and after a third week, it was increased to 15 mg/day in the 15 mg/day treatment arm (Study 2 in Table 26). All three doses of ABILIFY significantly improved scores on the ABC-I subscale compared with placebo.

Table 26: Irritability Associated with Autistic Disorder Studies (Pediatric)
Study Number | Treatment Group | Primary Efficacy Measure: ABC-I
Study Number | Treatment Group | Mean Baseline Score (SD) | LS Mean Change from Baseline (SE) | Placebo-subtracted Difference [Difference (drug minus placebo) in least-squares mean change from baseline.] (95% CI)
Study 1 | ABILIFY (2 to 15 mg/day) [Doses statistically significantly superior to placebo.] | 29.6 (6.37) | -12.9 (1.44) | -7.9 (-11.7, -4.1)
Study 1 | Placebo | 30.2 (6.52) | -5.0 (1.43) | --
Study 2 | ABILIFY (5 mg/day) | 28.6 (7.56) | -12.4 (1.36) | -4.0 (-7.7, -0.4)
Study 2 | ABILIFY (10 mg/day) | 28.2 (7.36) | -13.2 (1.25) | -4.8 (-8.4, -1.3)
Study 2 | ABILIFY (15 mg/day) | 28.9 (6.41) | -14.4 (1.31) | -6.0 (-9.6, -2.3)
Study 2 | Placebo | 28.0 (6.89) | -8.4 (1.39) | --
SD: standard deviation; SE: standard error; LS Mean: least-squares mean; CI: unadjusted confidence interval.

14.5 Tourette's Disorder

Pediatric Patients

The efficacy of ABILIFY in the treatment of Tourette's Disorder was established in one 8-week (7 to 17 years of age) and one 10-week (6 to 18 years of age), placebo-controlled trials in pediatric patients (6 to 18 years of age) who met the DSM-IV criteria for Tourette's Disorder and had a Total Tic score (TTS) ≥20 to 22 on the Yale Global Tic Severity Scale (YGTSS). The YGTSS is a fully validated scale designed to measure current tic severity. Efficacy was evaluated using two assessment scales: 1) the Total Tic score (TTS) of the YGTSS and 2) the Clinical Global Impressions Scale for Tourette's Syndrome (CGI-TS), a clinician-determined summary measure that takes into account all available patient information. Over 65% of these patients were under 13 years of age.

The primary outcome measure in both trials was the change from baseline to endpoint in the TTS of the YGTSS. Ratings for the TTS are made along 5 different dimensions on a scale of 0 to 5 for motor and vocal tics each. Summation of these 10 scores provides a TTS (i.e., 0 to 50).

The results of these trials are as follows:

In the 8-week, placebo-controlled, fixed-dose trial, children and adolescents with Tourette's Disorder (n=133), aged 7 to 17 years, were randomized 1:1:1 to low dose ABILIFY, high dose ABILIFY, or placebo. The target doses for the low and high dose ABILIFY groups were based on weight. Patients <50 kg in the low dose ABILIFY group started at 2 mg/day with a target dose of 5 mg/day after 2 days. Patients ≥50 kg in the low dose ABILIFY group, started at 2 mg/day increased to 5 mg/day after 2 days, with a subsequent increase to a target dose of 10 mg/day at Day 7. Patients <50 kg in the high dose ABILIFY group started at 2 mg/day increased to 5 mg/day after 2 days, with a subsequent increase to a target dose of 10 mg/day at Day 7. Patients ≥50 kg in the high dose ABILIFY group, started at 2 mg/day increased to 5 mg/day after 2 days, with a subsequent increase to a dose of 10 mg/day at Day 7 and were allowed weekly increases of 5 mg/day up to a target dose 20 mg/day at Day 21. ABILIFY (both high and low dose groups) demonstrated statistically significantly improved scores on the YGTSS TTS (Study 1 in Table 27) and on the CGI-TS scale compared with placebo. The estimated improvements on the YGTSS TTS over the course of the study are displayed in Figure 9.

Figure 9: Least Square Means of Change from Baseline in YGTSS TTS by Week (Tourette's Disorder Study 1)

In the 10-week, placebo-controlled, flexible-dose trial in children and adolescents with Tourette's Disorder (n=61), aged 6 to 18 years, patients received daily doses of placebo or ABILIFY, starting at 2 mg/day with increases allowed up to 20 mg/day based on clinical response. ABILIFY demonstrated statistically significantly improved scores on the YGTSS TTS scale compared with placebo (Study 2 in Table 27). The mean daily dose of ABILIFY at the end of 10-week treatment was 6.54 mg/day.

Table 27: Tourette's Disorder Studies (Pediatric)
Study Number | Treatment Group | Primary Efficacy Measure: YGTSS TTS
Study Number | Treatment Group | Mean Baseline Score (SD) | LS Mean Change from Baseline (SE) | Placebo-subtracted Difference [Difference (drug minus placebo) in least-squares mean change from baseline.] (95% CI)
Study 1 | ABILIFY (low dose) [Doses statistically significantly superior to placebo.] | 29.2 (5.63) | -13.4 (1.59) | -6.3 (-10.2, -2.3)
Study 1 | ABILIFY (high dose) | 31.2 (6.40) | -16.9 (1.61) | -9.9 (-13.8, -5.9)
Study 1 | Placebo | 30.7 (5.95) | -7.1 (1.55) | --
Study 2 | ABILIFY (2 to 20 mg/day) | 28.3 (5.51) | -15.0 (1.51) | -5.3 (-9.8, -0.9)
Study 2 | Placebo | 29.5 (5.60) | -9.6 (1.64) | --
SD: standard deviation; SE: standard error; LS Mean: least-squares mean; CI: unadjusted confidence interval.

16 HOW SUPPLIED/STORAGE AND HANDLING

How Supplied

ABILIFY® (aripiprazole) Tablets have markings on one side and are available in the strengths and packages listed in Table 28.

Table 28: ABILIFY Tablet Presentations
Tablet Strength | Tablet Color/Shape | Tablet Markings | Pack Size | NDC Code
2 mg | green modified rectangle | "A-006" and "2" | Bottle of 30 | 59148-006-13
5 mg | blue modified rectangle | "A-007" and "5" | Bottle of 30 Blister of 100 | 59148-007-13 59148-007-35
10 mg | pink modified rectangle | "A-008" and "10" | Bottle of 30 Blister of 100 | 59148-008-13 59148-008-35
15 mg | yellow round | "A-009" and "15" | Bottle of 30 Blister of 100 | 59148-009-13 59148-009-35
20 mg | white round | "A-010" and "20" | Bottle of 30 Blister of 100 | 59148-010-13 59148-010-35
30 mg | pink round | "A-011" and "30" | Bottle of 30 Blister of 100 | 59148-011-13 59148-011-35

Storage

Store at 25°C (77°F); excursions permitted between 15°C to 30°C (59°F to 86°F)[see USP Controlled Room Temperature].

17 PATIENT COUNSELING INFORMATION

Advise the patient to read the FDA-approved patient labeling (Medication Guide).

Clinical Worsening of Depression and Suicide Risk

Patients, their families, and their caregivers should be encouraged to be alert to the emergence of anxiety, agitation, panic attacks, insomnia, irritability, hostility, aggressiveness, impulsivity, akathisia (psychomotor restlessness), hypomania, mania, other unusual changes in behavior, worsening of depression, and suicidal ideation, especially early during antidepressant treatment and when the dose is adjusted up or down. Families and caregivers of patients should be advised to look for the emergence of such symptoms on a day-to-day basis, since changes may be abrupt. Such symptoms should be reported to the patient's prescriber or health professional, especially if they are severe, abrupt in onset, or were not part of the patient's presenting symptoms. Symptoms such as these may be associated with an increased risk for suicidal thinking and behavior and indicate a need for very close monitoring and possibly changes in the medication [see Warnings and Precautions (5.3)].

Prescribers or other health professionals should inform patients, their families, and their caregivers about the benefits and risks associated with treatment with ABILIFY and should counsel them in its appropriate use. A patient Medication Guide including information about "Antidepressant Medicines, Depression and other Serious Mental Illnesses, and Suicidal Thoughts or Actions" is available for ABILIFY. The prescriber or health professional should instruct patients, their families, and their caregivers to read the Medication Guide and should assist them in understanding its contents. Patients should be given the opportunity to discuss the contents of the Medication Guide and to obtain answers to any questions they may have. It should be noted that ABILIFY is not approved as a single agent for treatment of depression and has not been evaluated in pediatric major depressive disorder.

Pathological Gambling and Other Compulsive Behaviors

Advise patients and their caregivers of the possibility that they may experience compulsive urges to shop, intense urges to gamble, compulsive sexual urges, binge eating and/or other compulsive urges and the inability to control these urges while taking aripiprazole. In some cases, but not all, the urges were reported to have stopped when the dose was reduced or stopped [see Warnings and Precautions (5.7)].

Interference with Cognitive and Motor Performance

Because ABILIFY may have the potential to impair judgment, thinking, or motor skills, patients should be cautioned about operating hazardous machinery, including automobiles, until they are reasonably certain that ABILIFY therapy does not affect them adversely [see Warnings and Precautions (5.12)].

Concomitant Medication

Patients should be advised to inform their physicians if they are taking, or plan to take, any prescription or over-the-counter drugs, since there is a potential for interactions [see Drug Interactions (7)].

Heat Exposure and Dehydration

Patients should be advised regarding appropriate care in avoiding overheating and dehydration [see Warnings and Precautions (5.13)].

Pregnancy

Advise patients to notify their healthcare provider if they become pregnant or intend to become pregnant during treatment with ABILIFY. Advise patients that ABILIFY may cause extrapyramidal and/or withdrawal symptoms (agitation, hypertonia, hypotonia, tremor, somnolence, respiratory distress, and feeding disorder) in a neonate. Advise patients that there is a pregnancy registry that monitors pregnancy outcomes in women exposed to ABILIFY during pregnancy [see Use in Specific Populations (8.1)].

Lactation

Abilify use during pregnancy may affect milk supply. Advise the lactating patient to discuss any plans for breastfeeding with their healthcare provider, and to monitor the breastfed infant for dehydration and lack of appropriate weight gain [see Use in Specific Populations (8.2)].

Manufactured by Otsuka Pharmaceutical Co., Ltd., Tokyo, 101-8535 Japan

Distributed and Marketed by Otsuka America Pharmaceutical, Inc., Rockville, MD 20850 USA

ABILIFY is a registered trademark of Otsuka Pharmaceutical Co., Ltd.

© 2025 Otsuka Pharmaceutical Co., Ltd., Tokyo, 101-8535 Japan

MEDICATION GUIDE
ABILIFY® (a BIL ĭ fī)
(aripiprazole)
Tablets

What is the most important information I should know about ABILIFY?
(For other side effects, also see "What are the possible side effects of ABILIFY?")
Serious side effects may happen when you take ABILIFY, including:

- Increased risk of death in elderly patients with dementia-related psychosis: Medicines like ABILIFY can raise the risk of death in elderly people who have lost touch with reality (psychosis) due to confusion and memory loss (dementia). ABILIFY is not approved for the treatment of patients with dementia-related psychosis.
- Risk of suicidal thoughts or actions: Antidepressant medicines, depression and other serious mental illnesses, and suicidal thoughts or actions:
  - Antidepressant medicines may increase suicidal thoughts or actions in some children, teenagers, and young adults within the first few months of treatment.
  - Depression and other serious mental illnesses are the most important causes of suicidal thoughts and actions. Some people may have a particularly high risk of having suicidal thoughts or actions. These include people who have (or have a family history of) bipolar illness (also called manic-depressive illness) or suicidal thoughts or actions.
  - How can I watch for and try to prevent suicidal thoughts and actions in myself or a family member?
    - Pay close attention to any changes, especially sudden changes, in mood, behaviors, thoughts, or feelings. This is very important when an antidepressant medicine is started or when the dose is changed.
    - Call the healthcare provider right away to report new or sudden changes in mood, behavior, thoughts, or feelings.
    - Keep all follow-up visits with the healthcare provider as scheduled. Call the healthcare provider between visits as needed, especially if you have concerns about symptoms.

Call a healthcare provider right away if you or your family member has any of the following symptoms, especially if they are new, worse, or worry you:

- thoughts about suicide or dying
- attempts to commit suicide
- new or worse depression
- new or worse anxiety
- feeling very agitated or restless
- panic attacks
- trouble sleeping (insomnia)
- new or worse irritability
- acting aggressive, being angry, or violent
- acting on dangerous impulses
- an extreme increase in activity and talking (mania)
- other unusual changes in behavior or mood

What else do I need to know about antidepressant medicines?

- Never stop an antidepressant medicine without first talking to a healthcare provider. Stopping an antidepressant medicine suddenly can cause other symptoms.
- Antidepressants are medicines used to treat depression and other illnesses. It is important to discuss all the risks of treating depression and also the risks of not treating it. Patients and their families or other caregivers should discuss all treatment choices with the healthcare provider, not just the use of antidepressants.
- Antidepressant medicines have other side effects. Talk to the healthcare provider about the side effects of the medicine prescribed for you or your family member.
- Antidepressant medicines can interact with other medicines. Know all of the medicines that you or your family member take. Keep a list of all medicines to show the healthcare provider. Do not start new medicines without first checking with your healthcare provider.
- Not all antidepressant medicines prescribed for children are FDA approved for use in children. Talk to your child's healthcare provider for more information.

What is ABILIFY?

- ABILIFY is a prescription medicine used to treat:
  - schizophrenia
  - manic or mixed episodes that happen with bipolar I disorder
  - major depressive disorder (MDD) when ABILIFY is used with antidepressant medicines
  - irritability associated with autistic disorder
  - Tourette's Disorder

It is not known if ABILIFY is safe or effective in children:

- under 13 years of age with schizophrenia
- under 10 years of age with bipolar I disorder
- under 6 years of age with irritability associated with autistic disorder
- under 6 years of age with Tourette's Disorder

Do not take ABILIFY if you are allergic to aripiprazole or any of the ingredients in ABILIFY. See the end of this Medication Guide for a complete list of ingredients in ABILIFY.

Before taking ABILIFY, tell your healthcare provider about all your medical conditions, including if you have or had:

- diabetes or high blood sugar in you or your family; your healthcare provider should check your blood sugar before you start ABILIFY and also during therapy.
- seizures (convulsions).
- low or high blood pressure.
- heart problems or stroke.
- pregnancy or plans to become pregnant. It is not known if ABILIFY will harm your unborn baby.
  - If you become pregnant while receiving ABILIFY, talk to your healthcare provider about registering with the National Pregnancy Registry for Atypical Antipsychotics. You can register by calling 1-866-961-2388 or go to http://womensmentalhealth.org/clinical-and-research-programs/pregnancyregistry/
- breast-feeding or plans to breast-feed. ABILIFY passes into your breast milk. Talk to your healthcare provider about the best way to feed your baby if you receive ABILIFY.
- low white blood cell count.

Tell your healthcare provider about all the medicines that you take, including prescription and over-the-counter medicines, vitamins, and herbal supplements.
ABILIFY and other medicines may affect each other causing possible serious side effects. ABILIFY may affect the way other medicines work, and other medicines may affect how ABILIFY works.
Your healthcare provider can tell you if it is safe to take ABILIFY with your other medicines. Do not start or stop any medicines while taking ABILIFY without talking to your healthcare provider first. Know the medicines you take. Keep a list of your medicines to show your healthcare provider and pharmacist when you get a new medicine.

How should I take ABILIFY?

- Take ABILIFY exactly as your healthcare provider tells you to take it. Do not change the dose or stop taking ABILIFY yourself.
- ABILIFY can be taken with or without food.
- ABILIFY tablets should be swallowed whole.
- If you miss a dose of ABILIFY, take the missed dose as soon as you remember. If it is almost time for the next dose, just skip the missed dose and take your next dose at the regular time. Do not take two doses of ABILIFY at the same time.
- If you take too much ABILIFY, call your healthcare provider or poison control center at 1-800-222-1222 right away, or go to the nearest hospital emergency room.

What should I avoid while taking ABILIFY?

- Do not drive, operate heavy machinery, or do other dangerous activities until you know how ABILIFY affects you. ABILIFY may make you drowsy.
- Avoid getting over-heated or dehydrated.
  - Do not over-exercise.
  - In hot weather, stay inside in a cool place if possible.
  - Stay out of the sun. Do not wear too much or heavy clothing.
  - Drink plenty of water.

What are the possible side effects of ABILIFY?
ABILIFY may cause serious side effects, including:

- See "What is the most important information I should know about ABILIFY?"
- Stroke in elderly people (cerebrovascular problems) that can lead to death
- Neuroleptic malignant syndrome (NMS). Tell your healthcare provider right away if you have some or all of the following symptoms: high fever, stiff muscles, confusion, sweating, changes in pulse, heart rate, and blood pressure. These may be symptoms of a rare and serious condition that can lead to death. Call your healthcare provider right away if you have any of these symptoms.
- Uncontrolled body movements (tardive dyskinesia). ABILIFY may cause movements that you cannot control in your face, tongue, or other body parts. Tardive dyskinesia may not go away, even if you stop receiving ABILIFY. Tardive dyskinesia may also start after you stop receiving ABILIFY.
- Problems with your metabolism such as:
  - High blood sugar (hyperglycemia) and diabetes. Increases in blood sugar can happen in some people who take ABILIFY. Extremely high blood sugar can lead to coma or death. If you have diabetes or risk factors for diabetes (such as being overweight or a family history of diabetes), your healthcare provider should check your blood sugar before you start ABILIFY and during your treatment.
    Call your healthcare provider if you have any of these symptoms of high blood sugar while receiving ABILIFY:
    - feel very thirsty
    - need to urinate more than usual
    - feel very hungry
    - feel weak or tired
    - feel sick to your stomach
    - feel confused, or your breath smells fruity
  - Increased fat levels (cholesterol and triglycerides) in your blood.
  - Weight gain. You and your healthcare provider should check your weight regularly.
- Unusual urges. Some people taking ABILIFY have had unusual urges, such as gambling, binge eating or eating that you cannot control (compulsive), compulsive shopping and sexual urges.
  If you or your family members notice that you are having unusual urges or behaviors, talk to your healthcare provider.
- Orthostatic hypotension (decreased blood pressure). Lightheadedness or fainting may happen when rising too quickly from a sitting or lying position.
- Falls. ABILIFY may make you sleepy or dizzy, may cause a decrease in your blood pressure when changing position and can slow your thinking and motor skills which may lead to falls that can cause fractures or other injuries.
- Low white blood cell count
- Seizures (convulsions)
- Problems with control of your body temperature especially when you exercise a lot or are in an area that is very hot. It is important for you to drink water to avoid dehydration. See "What should I avoid while taking ABILIFY?"
- Difficulty swallowing that can cause food or liquid to get into your lungs.

The most common side effects of ABILIFY in adults include:

- nausea
- vomiting
- constipation
- headache
- blurred vision
- upper respiratory illness

- dizziness
- anxiety
- insomnia
- restlessness
- inner sense of restlessness/need to move (akathisia)

The most common side effects of ABILIFY in children include:

- feeling sleepy
- headache
- vomiting
- fatigue
- increased or decreased appetite
- increased saliva or drooling

- insomnia
- nausea
- stuffy nose
- weight gain
- uncontrolled movement such as restlessness, tremor
- muscle stiffness

These are not all the possible side effects of ABILIFY.
Call your doctor for medical advice about side effects. You may report side effects to FDA at 1-800-FDA-1088.

How should I store ABILIFY?
Store ABILIFY at room temperature, between 68°F to 77°F (20°C to 25°C).
Keep ABILIFY and all medicines out of the reach of children.

General information about the safe and effective use of ABILIFY
Medicines are sometimes prescribed for purposes other than those listed in a Medication Guide. Do not use ABILIFY for a condition for which it was not prescribed. Do not give ABILIFY to other people, even if they have the same symptoms you have. It may harm them. You can ask your healthcare provider or pharmacist for information about ABILIFY that was written for healthcare professionals.

What are the ingredients in ABILIFY?
Active ingredient: aripiprazole
Inactive ingredients:
Cornstarch, hydroxypropyl cellulose, lactose monohydrate, magnesium stearate, and microcrystalline cellulose. Colorants include ferric oxide (yellow or red) and FD&C Blue No. 2 Aluminum Lake
For more information about ABILIFY go to www.abilify.com or call 1-800-438-6055.
ABILIFY is a registered trademark of Otsuka Pharmaceutical Co., Ltd.
© 2025 Otsuka Pharmaceutical Co., Ltd., Tokyo, 101-8535 Japan

This Medication Guide has been approved by the U.S. Food and Drug Administration

Revised: 1/2025

PACKAGE/LABEL PRINCIPAL DISPLAY PANEL

30 Tablets NDC 59148-006-13
ABILIFY®
(aripiprazole)
TABLETS
2 mg
DISPENSE WITH MEDICATION GUIDE
Rx only
Otsuka America Pharmaceutical, Inc.

PACKAGE/LABEL PRINCIPAL DISPLAY PANEL

30 Tablets NDC 59148-007-13
ABILIFY®
(aripiprazole)
TABLETS
5 mg
DISPENSE WITH MEDICATION GUIDE
Rx only
Otsuka America Pharmaceutical, Inc.

PACKAGE/LABEL PRINCIPAL DISPLAY PANEL

30 Tablets NDC 59148-008-13
ABILIFY®
(aripiprazole)
TABLETS
10 mg
DISPENSE WITH MEDICATION GUIDE
Rx only
Otsuka America Pharmaceutical, Inc.

PACKAGE/LABEL PRINCIPAL DISPLAY PANEL

30 Tablets NDC 59148-009-13
ABILIFY®
(aripiprazole)
TABLETS
15 mg
DISPENSE WITH MEDICATION GUIDE
Rx only
Otsuka America Pharmaceutical, Inc.

PACKAGE/LABEL PRINCIPAL DISPLAY PANEL

30 Tablets NDC 59148-010-13
ABILIFY®
(aripiprazole)
TABLETS
20 mg
DISPENSE WITH MEDICATION GUIDE
Rx only
Otsuka America Pharmaceutical, Inc.

PACKAGE/LABEL PRINCIPAL DISPLAY PANEL

30 Tablets NDC 59148-011-13
ABILIFY®
(aripiprazole)
TABLETS
30 mg
DISPENSE WITH MEDICATION GUIDE
Rx only
Otsuka America Pharmaceutical, Inc.